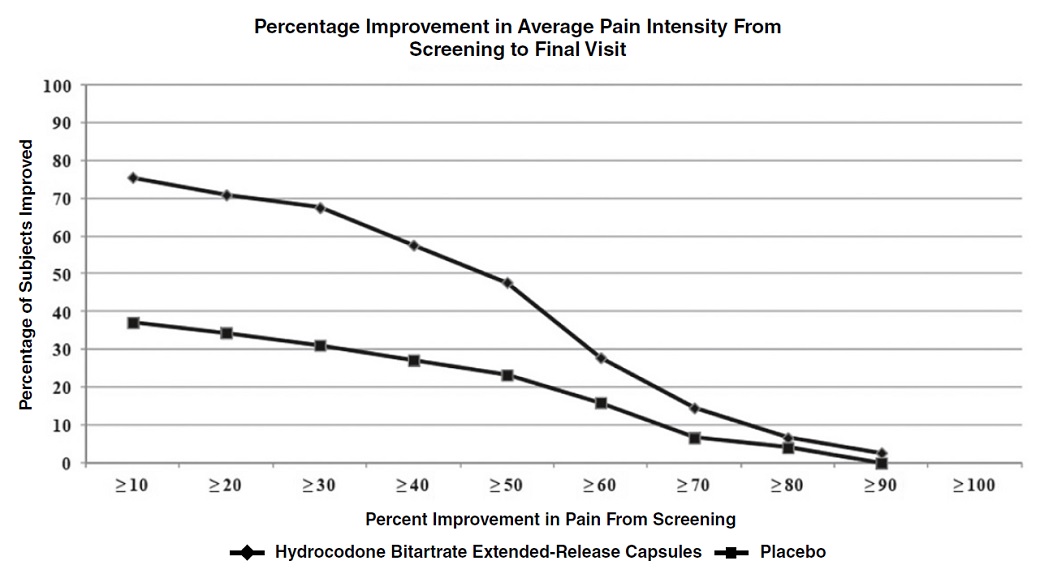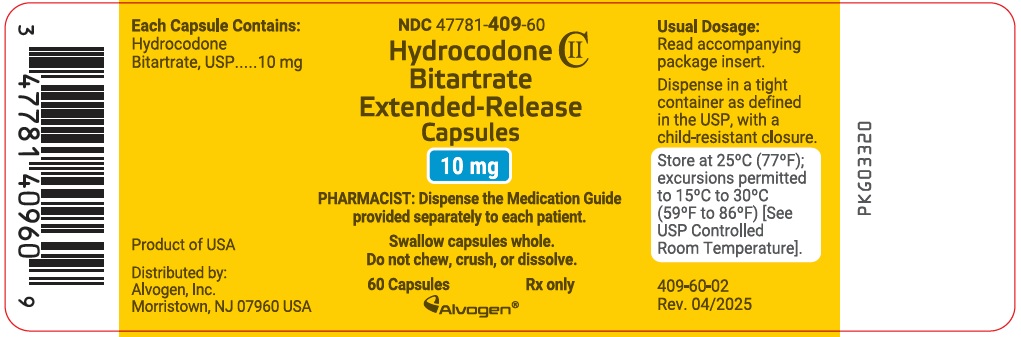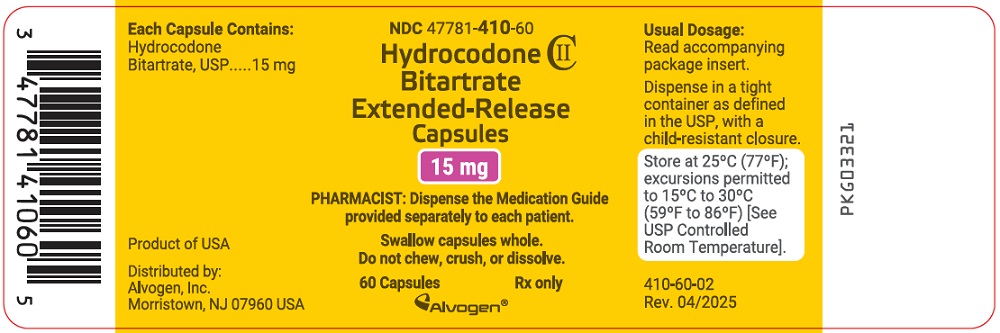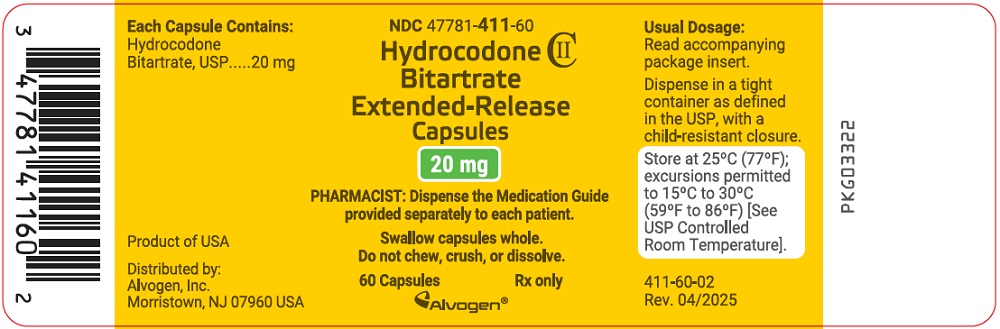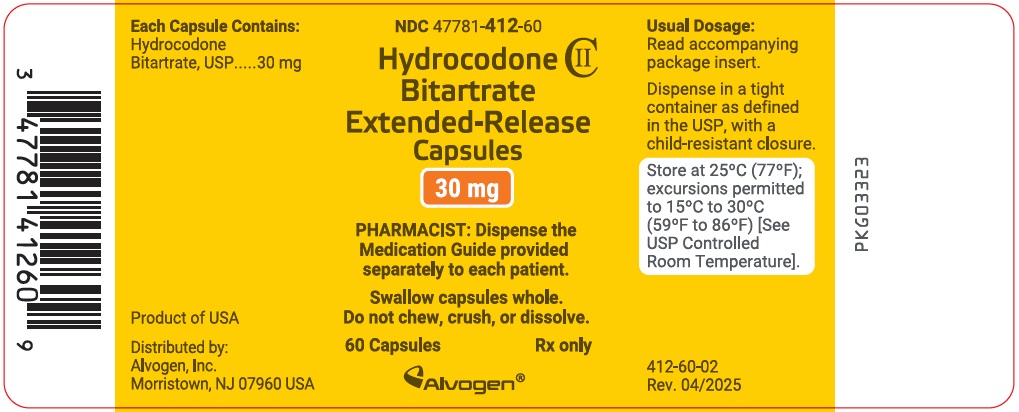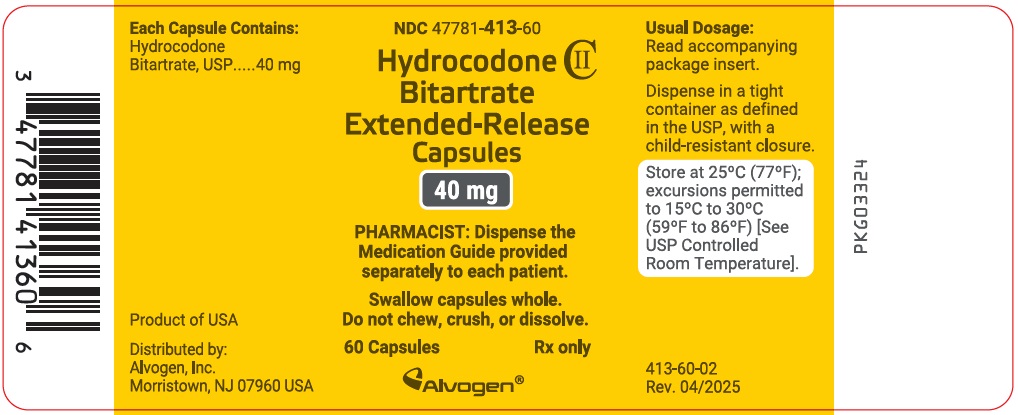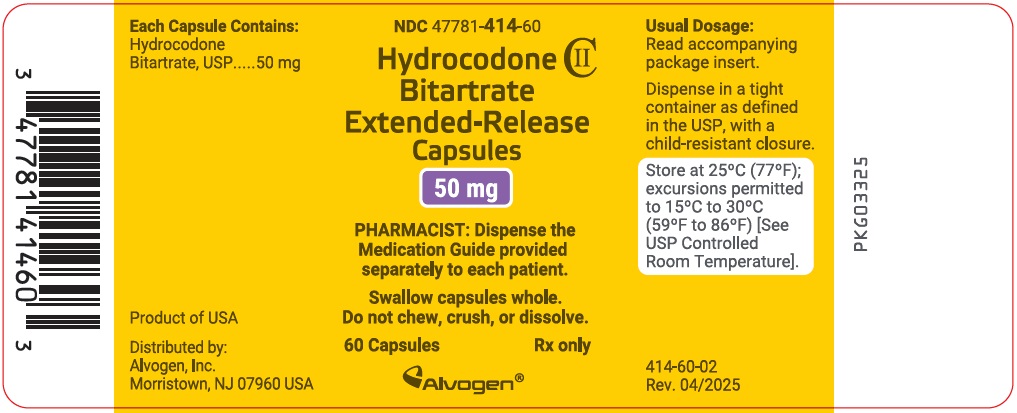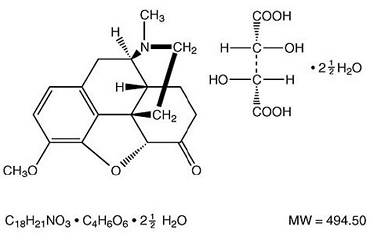 DRUG LABEL: Hydrocodone Bitartrate
NDC: 47781-409 | Form: CAPSULE, EXTENDED RELEASE
Manufacturer: Alvogen Inc.
Category: prescription | Type: HUMAN PRESCRIPTION DRUG LABEL
Date: 20231219
DEA Schedule: CII

ACTIVE INGREDIENTS: Hydrocodone Bitartrate 10 mg/1 1
INACTIVE INGREDIENTS: Sucrose; Ammonio Methacrylate Copolymer Type B; Silicon Dioxide; Talc; Titanium Dioxide; FD&C Blue No. 1; FD&C Red No. 40; Ferrosoferric Oxide; Gelatin, Unspecified; COPOVIDONE K25-31; Sodium Lauryl Sulfate; D&C Yellow No. 10; Fd&C Blue No. 2; Fd&C Yellow No. 6; Butyl Alcohol; PROPYLENE GLYCOL; Shellac

HIGHLIGHTS OF PRESCRIBING INFORMATION

These highlights do not include all the information needed to use HYDROCODONE BITARTRATE EXTENDED-RELEASE CAPSULES safely and effectively. See full prescribing information for HYDROCODONE BITARTRATE EXTENDED-RELEASE CAPSULES.
HYDROCODONE BITARTRATE extended-release capsules, for oral use, CII
Initial U.S. Approval: 1943

RECENT MAJOR CHANGES

Boxed Warning | 12/2023
Indications and Usage (1) | 12/2023
Dosage and Administration (2.1, 2.3, 2.4) | 12/2023
Warnings and Precautions (5.7) | 12/2023

WARNING: SERIOUS AND LIFE-THREATENING RISKS FROM USE OF HYDROCODONE BITARTRATE EXTENDED-RELEASE CAPSULES

See full prescribing information for complete boxed warning.

- Hydrocodone bitartrate extended-release capsules exposes users to risks of addiction, abuse, and misuse, which can lead to overdose and death. Assess patient’s risk before prescribing, and monitor regularly for these behaviors and conditions. (5.1)
- Serious, life-threatening, or fatal respiratory depression may occur. Monitor closely, especially upon initiation or following a dose increase. Instruct patients to swallow hydrocodone bitartrate extended-release capsules whole to avoid exposure to a potentially fatal dose of hydrocodone. (5.2)
- Accidental ingestion of hydrocodone bitartrate extended-release capsules, especially in children, can result in a fatal overdose of hydrocodone. (5.2)
- Concomitant use of opioids with benzodiazepines or other central nervous system (CNS) depressants, including alcohol, may result in profound sedation, respiratory depression, coma, and death. Reserve concomitant prescribing for use in patients for whom alternative treatment options are inadequate; limit dosages and durations to the minimum required; and follow patients for signs and symptoms of respiratory depression and sedation. (5.3, 7)
- Instruct patients not to consume alcohol or any products containing alcohol while taking hydrocodone bitartrate extended-release capsules because co-ingestion can result in fatal plasma hydrocodone levels. (5.3)
- Prolonged use of hydrocodone bitartrate extended-release capsules during pregnancy can result in neonatal opioid withdrawal syndrome, which may be life-threatening if not recognized and treated. If prolonged opioid use is required in a pregnant woman, advise the patient of the risk of neonatal opioid withdrawal syndrome and ensure that appropriate treatment will be available. (5.4)
- To ensure that the benefits of opioid analgesics outweigh the risks of addiction, abuse, and misuse, the Food and Drug Administration (FDA) has required a Risk Evaluation and Mitigation Strategy (REMS) for these products. (5.5)
- Concomitant use with CYP3A4 inhibitors (or discontinuation of CYP3A4 inducers) can result in a fatal overdose of hydrocodone. (5.6)

1 INDICATIONS AND USAGE

Hydrocodone bitartrate extended-release capsules are an opioid agonist indicated for the management of severe and persistent pain that requires an extended treatment period with a daily opioid analgesic and for which alternative treatment options are inadequate. (1)

Limitations of Use

- Because of the risks of addiction, abuse, and misuse with opioids, which can occur at any dosage or duration, and because of the greater risks of overdose and death with extended-release/long-acting opioid formulations, reserve hydrocodone bitartrate extended-release capsules for use in patients for whom alternative treatment options (e.g., non-opioid analgesics or immediate-release opioids) are ineffective, not tolerated, or would be otherwise inadequate to provide sufficient management of pain. (1)
- Hydrocodone bitartrate extended-release capsules are not indicated as an as-needed (prn) analgesic. (1)

2 DOSAGE AND ADMINISTRATION

- Hydrocodone bitartrate extended-release capsules should be prescribed only by healthcare professionals who are knowledgeable about the use of extended-release/long-acting opioids and how to mitigate the associated risks. (2.1)
- Daily doses of hydrocodone bitartrate extended-release capsules, a single dose greater than 40 mg, or a total daily dose greater than 80 mg are only for use in patients in whom tolerance to an opioid of comparable potency has been established. (2.1)
- Patients considered opioid-tolerant are those taking, for one week or longer, at least 60 mg oral morphine per day, 25 mcg transdermal fentanyl per hour, 30 mg oral oxycodone per day, 8 mg oral hydromorphone per day, 25 mg oral oxymorphone per day, 60 mg oral hydrocodone per day, or an equianalgesic dose of another opioid. (2.1)
- Use the lowest effective dosage for the shortest duration of time consistent with individual patient treatment goals. Reserve titration to higher doses of hydrocodone bitartrate extended-release capsules for patients in whom lower doses are insufficiently effective and in whom the expected benefits of using a higher dose opioid clearly outweigh the substantial risks. (2.1, 5)
- Initiate the dosing regimen for each patient individually, taking into account the patient’s underlying cause and severity of pain, prior analgesic treatment and response, and risk factors for addiction, abuse, and misuse. (2.1, 5.1)
- Respiratory depression can occur at any time during opioid therapy, especially when initiating and following dosage increases with hydrocodone bitartrate extended-release capsules. Consider this risk when selecting an initial dose and when making dose adjustments (2.1, 5.2)
- Instruct patients to swallow hydrocodone bitartrate extended-release capsules intact and not to cut, break, chew, crush, or dissolve the capsules (risk of potentially fatal overdose). (2.1, 5.1)
- Discuss availability of naloxone with the patient and caregiver and assess each patient’s need for access to naloxone, both when initiating and renewing treatment with hydrocodone bitartrate extended-release capsules. Consider prescribing naloxone based on the patient’s risk factors for overdose. (2.2, 5.1, 5.2, 5.3)
- For opioid-naïve and opioid non-tolerant patients, initiate with 10 mg capsules orally every 12 hours. (2.3)
- To convert to hydrocodone bitartrate extended-release capsules from another opioid, use available conversion factors to obtain estimated dose. (2.3)
- Dose titration of hydrocodone bitartrate extended-release capsules may occur every 3 to 7 days, using increments of 10 mg every 12 hours (i.e., 20 mg per day). (2.4)
- Patients with Severe Hepatic Impairment: Initiate dosing with 10 mg every 12 hours and titrate carefully, while monitoring for respiratory depression, sedation, and hypotension. No adjustment in starting dose with hydrocodone bitartrate extended-release capsules is required in patients with mild or moderate hepatic impairment. (2.5)
- Do not abruptly discontinue hydrocodone bitartrate extended-release capsules in a physically dependent patient. (2.6)

3 DOSAGE FORMS AND STRENGTHS

Extended-release capsules: 10 mg, 15 mg, 20 mg, 30 mg, 40 mg, and 50 mg (3)

4 CONTRAINDICATIONS

- Significant respiratory depression (4)
- Acute or severe bronchial asthma in an unmonitored setting or in the absence of resuscitative equipment (4)
- Known or suspected gastrointestinal obstruction, including paralytic ileus (4)
- Hypersensitivity to hydrocodone or to any other components of hydrocodone bitartrate extended-release capsules (4)

5 WARNINGS AND PRECAUTIONS

- Opioid-Induced Hyperalgesia and Allodynia: Opioid-Induced Hyperalgesia (OIH) occurs when an opioid analgesic paradoxically causes an increase in pain, or an increase in sensitivity to pain. If OIH is suspected, carefully consider appropriately decreasing the dose of the current opioid analgesic or opioid rotation. (5.7)
- Life-Threatening Respiratory Depression in Patients with Chronic Pulmonary Disease or in Elderly, Cachectic, or Debilitated Patients: Regularly evaluate, particularly during initiation and titration. (5.8)
- Adrenal Insufficiency: If diagnosed, treat with physiologic replacement of corticosteroids, and wean patient off of the opioid. (5.9)
- Severe Hypotension: Regularly evaluate during dosage initiation and titration. Avoid use of hydrocodone bitartrate extended-release capsules in patients with circulatory shock. (5.10)
- Risks of Use in Patients with Increased Intracranial Pressure, Brain Tumors, Head Injury, or Impaired Consciousness: Monitor for sedation and respiratory depression. Avoid use of hydrocodone bitartrate extended-release capsules in patients with impaired consciousness or coma. (5.11)

6 ADVERSE REACTIONS

Adverse reactions in ≥2% of patients in placebo-controlled trials include constipation, nausea, somnolence, fatigue, headache, dizziness, dry mouth, vomiting, pruritus, abdominal pain, edema peripheral, upper respiratory tract infection, muscle spasms, urinary tract infection, back pain, and tremor. (6.1)

To report SUSPECTED ADVERSE REACTIONS, contact Alvogen, Inc. at 1-866-770-3024 or FDA at 1-800-FDA-1088 or www.fda.gov/medwatch.

7 DRUG INTERACTIONS

- Serotonergic Drugs: Concomitant use may result in serotonin syndrome. Discontinue hydrocodone bitartrate extended-release capsules if serotonin syndrome is suspected. (7)
- Monoamine Oxidase Inhibitors (MAOIs): Can potentiate the effects of hydrocodone. Avoid concomitant use in patients receiving MAOIs or within 14 days of stopping an MAOI. (7)
- Mixed Agonists/Antagonists and Partial Agonist Opioid Analgesics: Avoid use with hydrocodone bitartrate extended-release capsules because they may reduce analgesic effect of hydrocodone bitartrate extended-release capsules or precipitate withdrawal symptoms. (7)

8 USE IN SPECIFIC POPULATIONS

- Pregnancy: May cause fetal harm. (8.1)
- Lactation: Not recommended. (8.2)

FULL PRESCRIBING INFORMATION

WARNING: SERIOUS AND LIFE-THREATENING RISKS FROM USE OF HYDROCODONE BITARTRATE EXTENDED-RELEASE CAPSULES

Addiction, Abuse, and Misuse

Because the use of hydrocodone bitartrate extended-release capsules exposes patients and other users to the risks of opioid addiction, abuse, and misuse, which can lead to overdose and death, assess each patient’s risk prior to prescribing and reassess all patients regularly for the development of these behaviors and conditions [see Warnings and Precautions (5.1)].

Life-Threatening Respiratory Depression

Serious, life-threatening, or fatal respiratory depression may occur with use of hydrocodone bitartrate extended-release capsules, especially during initiation or following a dosage increase. To reduce the risk of respiratory depression, proper dosing and titration of hydrocodone bitartrate extended-release capsules are essential. Instruct patients to swallow hydrocodone bitartrate extended-release capsules whole; crushing, chewing, or dissolving hydrocodone bitartrate extended-release capsules can cause rapid release and absorption of a potentially fatal dose of hydrocodone [see Warnings and Precautions (5.2)].

Accidental Ingestion

Accidental ingestion of even one dose of hydrocodone bitartrate extended-release capsules, especially by children, can result in a fatal overdose of hydrocodone [see Warnings and Precautions (5.2)].

Risks From Concomitant Use with Benzodiazepines or Other CNS Depressants

Concomitant use of opioids with benzodiazepines or other central nervous system (CNS) depressants, including alcohol, may result in profound sedation, respiratory depression, coma, and death. Reserve concomitant prescribing of hydrocodone bitartrate extended-release capsules and benzodiazepines or other CNS depressants for use in patients for whom alternative treatment options are inadequate [see Warnings and Precautions (5.3), Drug Interactions (7)].

Interaction with Alcohol

Instruct patients not to consume alcoholic beverages or use prescription or non-prescription products that contain alcohol while taking hydrocodone bitartrate extended-release capsules. The co-ingestion of alcohol with hydrocodone bitartrate extended-release capsules may result in increased plasma levels and a potentially fatal overdose of hydrocodone [see Warnings and Precautions (5.3) and Clinical Pharmacology (12.3)].

Neonatal Opioid Withdrawal Syndrome (NOWS)

If opioid use is required for an extended period of time in a pregnant woman, advise the patient of the risk of NOWS, which may be life-threatening if not recognized and treated. Ensure that management by neonatology experts will be available at delivery [see Warnings and Precautions (5.4)].

Opioid Analgesic Risk Evaluation and Mitigation Strategy (REMS)

Healthcare providers are strongly encouraged to complete a REMS-compliant education program and to counsel patients and caregivers on serious risks, safe use, and the importance of reading the Medication Guide with each prescription [see Warnings and Precautions (5.5)].

Cytochrome P450 3A4 Interaction

The concomitant use of hydrocodone bitartrate extended-release capsules with all cytochrome P450 3A4 inhibitors may result in an increase in hydrocodone plasma concentrations, which could increase or prolong adverse drug effects and may cause potentially fatal respiratory depression. In addition, discontinuation of a concomitantly used cytochrome P450 3A4 inducer may result in an increase in hydrocodone plasma concentration. Monitor patients receiving hydrocodone bitartrate extended-release capsules and any CYP3A4 inhibitor or inducer [see Warnings and Precautions (5.6) and Clinical Pharmacology (12.3)].

1 INDICATIONS AND USAGE

Hydrocodone bitartrate extended-release capsules are indicated for the management of severe and persistent pain that requires an extended treatment period with a daily opioid analgesic and for which alternative treatment options are inadequate.

Limitations of Use:

- Because of the risks of addiction, abuse, and misuse with opioids, which can occur at any dosage or duration, and because of the greater risks of overdose and death with extended-release/long-acting opioid formulations, [see Warnings and Precautions (5.1)], reserve hydrocodone bitartrate extended-release capsules for use in patients for whom alternative treatment options (e.g., non-opioid analgesics or immediate-release opioids) are ineffective, not tolerated, or would be otherwise inadequate to provide sufficient management of pain.
- Hydrocodone bitartrate extended-release capsules are not indicated as an as-needed (prn) analgesic.

2 DOSAGE AND ADMINISTRATION

2.1 Important Dosage and Administration Information

Hydrocodone bitartrate extended-release capsules should be prescribed only by healthcare professionals who are knowledgeable about the use of extended-release/long-acting opioids and how to mitigate the associated risks.

Daily doses of hydrocodone bitartrate extended-release capsules, a single dose of greater than 40 mg, or a total daily dose of greater than 80 mg, are only for use in patients in whom tolerance to an opioid of comparable potency has been established. Patients who are opioid tolerant are those receiving, for one week or longer, at least 60 mg oral morphine per day, 25 mcg transdermal fentanyl per hour, 30 mg oral oxycodone per day, 8 mg oral hydromorphone per day, 25 mg oral oxymorphone per day, 60 mg oral hydrocodone per day, or an equianalgesic dose of another opioid.

Use the lowest effective dosage for the shortest duration of time consistent with individual patient treatment goals [see Warnings and Precautions (5)]. Because the risk of overdose increases as opioid doses increase, reserve titration to higher doses of hydrocodone bitartrate extended-release capsules for patients in whom lower doses are insufficiently effective and in whom the expected benefits of using a higher dose opioid clearly outweigh the substantial risks.

Initiate the dosing regimen for each patient individually, taking into account the patient's underlying cause and severity of pain, prior analgesic treatment and response, and risk factors for addiction, abuse, and misuse [see Warnings and Precautions (5.1)].

Respiratory depression can occur at any time during opioid therapy, especially when initiating and following dosage increases with hydrocodone bitartrate extended-release capsules. Consider this risk when selecting an initial dose and when making dose adjustments [see Warnings and Precautions (5)].

Instruct patients to swallow hydrocodone bitartrate extended-release capsules whole [see Patient Counseling Information (17)]. Crushing, chewing, or dissolving the beads in hydrocodone bitartrate extended-release capsules will result in uncontrolled delivery of hydrocodone and can lead to overdose or death [see Warnings and Precautions (5.1)].

Hydrocodone bitartrate extended-release capsules are administered orally twice daily (every 12 hours).

2.2 Patient Access to Naloxone for the Emergency Treatment of Opioid Overdose

Discuss the availability of naloxone for the emergency treatment of opioid overdose with the patient and caregiver and assess the potential need for access to naloxone, both when initiating and renewing treatment with hydrocodone bitartrate extended-release capsules [see Warnings and Precautions (5.2), Patient Counseling Information (17)].

Inform patients and caregivers about the various ways to obtain naloxone as permitted by individual state naloxone dispensing and prescribing requirements or guidelines (e.g., by prescription, directly from a pharmacist, or as part of a community-based program).

Consider prescribing naloxone, based on the patient’s risk factors for overdose, such as concomitant use of CNS depressants, a history of opioid use disorder, or prior opioid overdose. The presence of risk factors for overdose should not prevent the proper management of pain in any given patient [see Warnings and Precautions (5.1, 5.2, 5.3)].

Consider prescribing naloxone if the patient has household members (including children) or other close contacts at risk for accidental ingestion or overdose.

2.3 Initial Dosage

Use of Hydrocodone Bitartrate Extended-Release Capsules as the First Opioid Analgesic (opioid-naïve patients)

Initiate therapy with hydrocodone bitartrate extended-release capsules with one 10 mg capsule every 12 hours.

Use of Hydrocodone Bitartrate Extended-Release Capsules in Patients Who Are Not Opioid Tolerant

The starting dose for patients who are not opioid tolerant is hydrocodone bitartrate extended-release capsules 10 mg orally every 12 hours.

Use of higher starting doses in patients who are not opioid tolerant may cause fatal respiratory depression [see Warnings and Precautions (5.2)].

Conversion from Oral Hydrocodone Formulations to Hydrocodone Bitartrate Extended-Release Capsules

Patients receiving other oral hydrocodone-containing formulations may be converted to hydrocodone bitartrate extended-release capsules by dividing the patient’s total daily oral hydrocodone dose in half and administrating as hydrocodone bitartrate extended-release capsules every 12 hours.

Conversion from Other Oral Opioids to Hydrocodone Bitartrate Extended-Release Capsules

When hydrocodone bitartrate extended-release capsules therapy is initiated, discontinue all other opioid analgesics other than those used on an as needed basis for breakthrough pain when appropriate.

There is inter-patient variability in the relative potency of different opioid drugs and products. Therefore, a conservative approach is advised when determining the total daily dosage of hydrocodone bitartrate extended-release capsules. It is safer to underestimate a patient's 24-hour oral hydrocodone dosage and provide rescue medication (e.g., immediate-release opioid) than to overestimate the 24-hour oral hydrocodone dosage and manage an adverse reaction due to an overdose.

In a hydrocodone bitartrate extended-release capsules clinical trial with an open label titration period, patients were converted from their prior opioid to hydrocodone bitartrate extended-release capsules using Table 1 as a guide for the initial hydrocodone bitartrate extended-release capsules dose. To obtain the initial hydrocodone bitartrate extended-release capsules dose, first use Table 1 to convert the prior oral opioids to a total hydrocodone daily dose and then reduce the calculated daily hydrocodone dose by 25% to account for interpatient variability in relative potency of different opioids.

Consider the following when using the information in Table 1:

- This is not a table of equianalgesic doses.
- The conversion factors in this table are only for the conversion from one of the listed oral opioid analgesics to hydrocodone bitartrate extended-release capsules.
- The table cannot be used to convert from hydrocodone bitartrate extended-release capsules to another opioid. Doing so will result in an over-estimation of the dose of the new opioid and may result in fatal overdose.

Table 1. Conversion Factors to Hydrocodone Bitartrate Extended-Release Capsules (Not Equianalgesic Doses)
Prior Oral Opioid | Oral Dose (mg) | Approximate Oral Conversion Factor
Hydrocodone | 10 | 1
Oxycodone | 10 | 1
Methadone | 10 | 1
Oxymorphone | 5 | 2
Hydromorphone | 3.75 | 2.67
Morphine | 15 | 0.67
Codeine | 100 | 0.10
The conversion ratios in this table are only to be used for the conversion from current opioid therapy to hydrocodone bitartrate extended-release capsules.

To calculate the estimated daily hydrocodone bitartrate extended-release capsule dose using Table 1:

- For patients on a single opioid, sum the current total daily dose of the opioid and then multiply the total daily dose by the approximate oral conversion factor to calculate the approximate oral hydrocodone daily dose. Divide the daily dose in half for administration every 12 hours.
- For patients on a regimen of more than one opioid, calculate the approximate oral hydrocodone dose for each opioid and sum the totals to obtain approximate total hydrocodone daily dose. The daily dose should then be divided in half for administration every 12 hours.
- For patients on a regimen of fixed-ratio opioid/non-opioid analgesic products, use only the opioid component of these products in the conversion.
- Reduce the calculated daily oral hydrocodone dose by 25%.

Always round the dose down, if necessary, to the nearest hydrocodone bitartrate extended-release capsule strength(s) available and initiate therapy with that dose.

Example conversion from a single opioid to hydrocodone bitartrate extended-release capsules

Step 1: Sum the total daily dose of the opioid (in this case, extended-release oxymorphone); 15 mg oxymorphone twice daily = 30 mg total daily dose of oxymorphone.

Step 2: Calculate the approximate equivalent dose of oral hydrocodone based on the total daily dose of the current opioid using Table 1; 30 mg total daily dose of oxymorphone x 2 = 60 mg of oral hydrocodone daily. The daily dose should then be divided in half for administration every 12 hours.

Step 3: Calculate the approximate starting dose which is 30 mg hydrocodone bitartrate extended-release capsules every 12 hours. Round down, if necessary, to the appropriate hydrocodone bitartrate extended-release capsule strengths available. Close observation and frequent titration are warranted until pain management is stable on the new opioid. Monitor patients for signs and symptoms of opioid withdrawal or for signs of over-sedation/toxicity after converting patients to hydrocodone bitartrate extended-release capsules.

The dose of hydrocodone bitartrate extended-release capsules can be gradually adjusted preferably at increments of 10 mg every 12 hours every 3 to 7 days, until adequate pain relief and acceptable adverse reactions have been achieved.

Conversion from Methadone to Hydrocodone Bitartrate Extended-Release Capsules

Close monitoring is of particular importance when converting from methadone to other opioid agonists. The ratio between methadone and other opioid agonists may vary widely as a function of previous dose exposure. Methadone has a long half-life and tends to accumulate in the plasma.

Conversion from Transdermal Fentanyl to Hydrocodone Bitartrate Extended-Release Capsules

Hydrocodone bitartrate extended-release capsules treatment can be initiated 18 hours following the removal of the transdermal fentanyl patch. Although there has been no systematic assessment of such conversion, a conservative hydrocodone dose, approximately 10 mg every 12 hours of hydrocodone bitartrate extended-release capsules, should be initially substituted for each 25 mcg/hr fentanyl transdermal patch. Follow the patient closely during conversion from transdermal fentanyl to hydrocodone bitartrate extended-release capsules, as there is limited documented experience with this conversion.

2.4 Titration and Maintenance of Therapy

Individually titrate hydrocodone bitartrate extended-release capsules to a dose that provides adequate analgesia and minimizes adverse reactions. Continually reevaluate patients receiving hydrocodone bitartrate extended-release capsules to assess the maintenance of pain control, signs and symptoms of opioid withdrawal, and other adverse reactions, as well as to reassess for the development of addiction, abuse, or misuse [see Warnings and Precautions (5.1, 5.14)]. Frequent communication is important among the prescriber, other members of the healthcare team, the patient, and the caregiver/family during periods of changing analgesic requirements, including initial titration. During use of opioid therapy for an extended period of time, periodically reassess the continued need for use of opioid analgesics.

Patients who experience breakthrough pain may require a dosage adjustment of hydrocodone bitartrate extended-release capsules, or may need a rescue medication with an appropriate dose of an immediate-release analgesic. If the level of pain increases after dose stabilization, attempt to identify the source of increased pain before increasing the hydrocodone bitartrate extended-release capsules dosage. Because steady-state plasma concentrations are approximated within 3 days, hydrocodone bitartrate extended-release capsules dosage adjustments, preferably at increments of 10 mg every 12 hours, may be done every 3 to 7 days.

If after increasing the dosage, unacceptable opioid-related adverse reactions are observed (including an increase in pain after dosage increase), consider reducing the dosage [see Warnings and Precautions (5)]. Adjust the dosage to obtain an appropriate balance between management of pain and opioid-related adverse reactions.

2.5 Dosage Modifications in Patients with Severe Hepatic Impairment

Patients with severe hepatic impairment may have higher plasma concentrations of hydrocodone than those with normal function. Therefore, initiate therapy with 10 mg every 12 hours and titrate carefully, while monitoring for respiratory depression, sedation, and hypotension. No adjustment in starting dose with hydrocodone bitartrate extended-release capsules is required in patients with mild or moderate hepatic impairment [see Clinical Pharmacology (12.3)].

2.6 Safe Reduction or Discontinuation of Hydrocodone Bitartrate Extended-Release Capsules

Do not abruptly discontinue hydrocodone bitartrate extended-release capsules in patients who may be physically dependent on opioids. Rapid discontinuation of opioid analgesics in patients who are physically dependent on opioids has resulted in serious withdrawal symptoms, uncontrolled pain, and suicide. Rapid discontinuation has also been associated with attempts to find other sources of opioid analgesics, which may be confused with drug-seeking for abuse. Patients may also attempt to treat their pain or withdrawal symptoms with illicit opioids, such as heroin, and other substances.

When a decision has been made to decrease the dose or discontinue therapy in an opioid-dependent patient taking hydrocodone bitartrate extended-release capsules, there are a variety of factors that should be considered, including the total daily dose of opioid (including hydrocodone bitartrate extended-release capsules) the patient has been taking, the duration of treatment, the type of pain being treated, and the physical and psychological attributes of the patient. It is important to ensure ongoing care of the patient and to agree on an appropriate tapering schedule and follow-up plan so that patient and provider goals and expectations are clear and realistic. When opioid analgesics are being discontinued due to a suspected substance use disorder, evaluate and treat the patient, or refer for evaluation and treatment of the substance use disorder.

Treatment should include evidence-based approaches, such as medication assisted treatment of opioid use disorder. Complex patients with co- morbid pain and substance use disorders may benefit from referral to a specialist.

There are no standard opioid tapering schedules that are suitable for all patients. Good clinical practice dictates a patient-specific plan to taper the dose of the opioid gradually. For patients on hydrocodone bitartrate extended-release capsules who are physically opioid-dependent, initiate the taper by a small enough increment (e.g., no greater than 10% to 25% of the total daily dose) to avoid withdrawal symptoms, and proceed with dose-lowering at an interval of every 2 to 4 weeks. Patients who have been taking opioids for briefer periods of time may tolerate a more rapid taper.

It may be necessary to provide the patient with lower dosage strengths to accomplish a successful taper. Reassess the patient frequently to manage pain and withdrawal symptoms, should they emerge. Common withdrawal symptoms include restlessness, lacrimation, rhinorrhea, yawning, perspiration, chills, myalgia, and mydriasis. Other signs and symptoms also may develop, including irritability, anxiety, backache, joint pain, weakness, abdominal cramps, insomnia, nausea, anorexia, vomiting, diarrhea, or increased blood pressure, respiratory rate, or heart rate. If withdrawal symptoms arise, it may be necessary to pause the taper for a period of time or raise the dose of the opioid analgesic to the previous dose, and then proceed with a slower taper. In addition, evaluate patients for any changes in mood, emergence of suicidal thoughts, or use of other substances.

When managing patients taking opioid analgesics, particularly those who have been treated for an extended period of time, and/or with high doses for chronic pain, ensure that a multimodal approach to pain management, including mental health support (if needed), is in place prior to initiating an opioid analgesic taper. A multimodal approach to pain management may optimize the treatment of chronic pain, as well as assist with the successful tapering of the opioid analgesic [see Warnings and Precautions (5.14), Drug Abuse and Dependence (9.3)].

3 DOSAGE FORMS AND STRENGTHS

10 mg | Light blue cap and yellow body | "ALV" printed on the cap and "409" printed on the body in grey ink
15 mg | Light lavender cap and yellow body | "ALV" printed on the cap and "410" printed on the body in grey ink
20 mg | White cap and yellow body | "ALV" printed on the cap and "411" printed on the body in grey ink
30 mg | Light pink cap and yellow body | "ALV" printed on the cap and "412" printed on the body in grey ink
40 mg | Yellow cap and yellow body | "ALV" printed on the cap and "413" printed on the body in grey ink
50 mg | Light grey cap and yellow body | "ALV" printed on the cap and "414" printed on the body in grey ink

4 CONTRAINDICATIONS

Hydrocodone bitartrate extended-release capsules are contraindicated in patients with:

- Significant respiratory depression [see Warnings and Precautions (5.2)]
- Acute or severe bronchial asthma in an unmonitored setting or in the absence of resuscitative equipment [see Warnings and Precautions (5.8)]
- Known or suspected gastrointestinal obstruction, including paralytic ileus [see Warnings and Precautions (5.12)]
- Hypersensitivity (e.g., anaphylaxis) to hydrocodone or any other ingredients in hydrocodone bitartrate extended-release capsules

5 WARNINGS AND PRECAUTIONS

5.1 Addiction, Abuse, and Misuse

Hydrocodone bitartrate extended-release capsules contain hydrocodone, a Schedule II controlled substance. As an opioid, hydrocodone bitartrate extended-release capsules exposes users to the risks of addiction, abuse, and misuse. Because extended-release products such as hydrocodone bitartrate extended-release capsules deliver the opioid over an extended period of time, there is a greater risk for overdose and death due to the larger amount of hydrocodone present [see Drug Abuse and Dependence (9.1)].

Although the risk of addiction in any individual is unknown, it can occur in patients appropriately prescribed hydrocodone bitartrate extended-release capsules. Addiction can occur at recommended doses and if the drug is misused or abused.

Assess each patient’s risk for opioid addiction, abuse, or misuse prior to prescribing hydrocodone bitartrate extended-release capsules, and reassess all patients receiving hydrocodone bitartrate extended-release capsules for the development of these behaviors and conditions. Risks are increased in patients with a personal or family history of substance abuse (including drug or alcohol addiction or abuse) or mental illness (e.g., major depression). The potential for these risks should not, however, prevent the prescribing of hydrocodone bitartrate extended-release capsules for the proper management of pain in any given patient. Patients at increased risk may be prescribed opioids such as hydrocodone bitartrate extended-release capsules, but use in such patients necessitates intensive counseling about the risks and proper use of hydrocodone bitartrate extended-release capsules along with frequent reevaluation for signs of addiction, abuse, and misuse. Consider prescribing naloxone for the emergency treatment of opioid overdose [see Dosage and Administration (2.2), Warnings and Precautions (5.2)].

Abuse or misuse of hydrocodone bitartrate extended-release capsules by crushing, chewing, snorting, or injecting the dissolved product will result in the uncontrolled delivery of the hydrocodone and can result in overdose and death [see Drug Abuse and Dependence (9.1), Overdosage (10)].

Opioids are sought for nonmedical use and are subject to diversion from legitimate prescribed use. Consider these risks when prescribing or dispensing hydrocodone bitartrate extended-release capsules. Strategies to reduce these risks include prescribing the drug in the smallest appropriate quantity and advising the patient on careful storage of the drug during the course of treatment and proper disposal of unused drug. Contact local state professional licensing board or state-controlled substances authority for information on how to prevent and detect abuse or diversion of this product.

5.2 Life-Threatening Respiratory Depression

Serious, life-threatening, or fatal respiratory depression has been reported with the use of opioids, even when used as recommended. Respiratory depression, if not immediately recognized and treated, may lead to respiratory arrest and death. Management of respiratory depression may include close observation, supportive measures, and use of opioid antagonists, depending on the patient's clinical status [see Overdosage (10)]. Carbon dioxide (CO2) retention from opioid-induced respiratory depression can exacerbate the sedating effects of opioids.

While serious, life-threatening, or fatal respiratory depression can occur at any time during the use of hydrocodone bitartrate extended-release capsules, the risk is greatest during the initiation of therapy or following a dosage increase.

To reduce the risk of respiratory depression, proper dosing and titration of hydrocodone bitartrate extended-release capsules are essential [see Dosage and Administration (2.4)]. Overestimating the hydrocodone bitartrate extended-release capsules dose when converting patients from another opioid product can result in fatal overdose with the first dose.

Accidental ingestion of even one dose of hydrocodone bitartrate extended-release capsules, especially by children, can result in respiratory depression and death due to an overdose of hydrocodone.

Educate patients and caregivers on how to recognize respiratory depression and emphasize the importance of calling 911 or getting emergency medical help right away in the event of a known or suspected overdose [see Patient Counseling Information (17)].

Opioids can cause sleep-related breathing disorders including central sleep apnea (CSA) and sleep-related hypoxemia. Opioid use increases the risk of CSA in a dose-dependent fashion. In patients who present with CSA, consider decreasing the opioid dosage using best practices for opioid taper [see Dosage and Administration (2.6)].

Patient Access to Naloxone for the Emergency Treatment of Opioid Overdose

Discuss the availability of naloxone for the emergency treatment of opioid overdose with the patient and caregiver and assess the potential need for access to naloxone, both when initiating and renewing treatment with hydrocodone bitartrate extended-release capsules. Inform patients and caregivers about the various ways to obtain naloxone as permitted by individual state naloxone dispensing and prescribing requirements or guidelines (e.g., by prescription, directly from a pharmacist, or as part of a community-based program). Educate patients and caregivers on how to recognize respiratory depression and emphasize the importance of calling 911 or getting emergency medical help, even if naloxone is administered [see Patient Counseling Information (17)].

Consider prescribing naloxone, based on the patient’s risk factors for overdose, such as concomitant use of CNS depressants, a history of opioid use disorder, or prior opioid overdose. The presence of risk factors for overdose should not prevent the proper management of pain in any given patient. Also consider prescribing naloxone if the patient has household members (including children) or other close contacts at risk for accidental ingestion or overdose. If naloxone is prescribed, educate patients and caregivers on how to treat with naloxone [see Dosage and Administration (2.2), Warnings and Precautions (5.1, 5.3), Overdosage (10)].

5.3 Risks from Concomitant Use with Benzodiazepines or Other CNS Depressants

Profound sedation, respiratory depression, coma, and death may result from the concomitant use of hydrocodone bitartrate extended-release capsules with benzodiazepines and/or other CNS depressants, including alcohol (e.g., non-benzodiazepine sedatives/hypnotics, anxiolytics, tranquilizers, muscle relaxants, general anesthetics, antipsychotics, other opioids). Because of these risks, reserve concomitant prescribing of these drugs for use in patients for whom alternative treatment options are inadequate.

Observational studies have demonstrated that concomitant use of opioid analgesics and benzodiazepines increases the risk of drug-related mortality compared to use of opioid analgesics alone. Because of similar pharmacological properties, it is reasonable to expect similar risk with the concomitant use of other CNS depressant drugs with opioid analgesics [see Drug Interactions (7)].

If the decision is made to prescribe a benzodiazepine or other CNS depressant concomitantly with an opioid analgesic, prescribe the lowest effective dosages and minimum duration of concomitant use. In patients already receiving an opioid analgesic, prescribe a lower initial dose of the benzodiazepine or other CNS depressant than indicated in the absence of an opioid, and titrate based on clinical response. If an opioid analgesic is initiated in a patient already taking a benzodiazepine or other CNS depressant, prescribe a lower initial dose of the opioid analgesic, and titrate based on clinical response. Inform patients and caregivers of this potential interaction, educate them on the signs and symptoms of respiratory depression (including sedation).

If concomitant use is warranted, consider prescribing naloxone for the emergency treatment of opioid overdose [see Dosage and Administration (2.2), Warnings and Precautions (5.2)].

Advise both patients and caregivers about the risks of respiratory depression and sedation when hydrocodone bitartrate extended-release capsules is used with benzodiazepines or other CNS depressants (including alcohol and illicit drugs). Advise patients not to drive or operate heavy machinery until the effects of concomitant use of the benzodiazepine or other CNS depressant have been determined. Screen patients for risk of substance use disorders, including opioid abuse and misuse, and warn them of the risk of overdose and death associated with the use of additional CNS depressants including alcohol and illicit drugs [see Drug Interactions (7) and Patient Counseling Information (17)].

Patients must not consume alcoholic beverages, or prescription or non-prescription products containing alcohol, while on hydrocodone bitartrate extended-release capsules therapy. The co-ingestion of alcohol with hydrocodone bitartrate extended-release capsules may result in increased plasma levels and a potentially fatal overdose of hydrocodone [see Clinical Pharmacology (12.3)].

5.4 Neonatal Opioid Withdrawal Syndrome

Use of hydrocodone bitartrate extended-release capsules for an extended period of time during pregnancy can result in withdrawal in the neonate. Neonatal opioid withdrawal syndrome, unlike opioid withdrawal syndrome in adults, may be life-threatening if not recognized and treated, and requires management according to protocols developed by neonatology experts. Observe newborns for signs of neonatal opioid withdrawal syndrome and manage accordingly. Advise pregnant women using opioids for an extended period of time of the risk of neonatal opioid withdrawal syndrome and ensure that appropriate treatment will be available [see Use in Specific Populations (8.1), Patient Counseling Information (17)].

5.5 Opioid Analgesic Risk Evaluation and Mitigation Strategy (REMS)

To ensure that the benefits of opioid analgesics outweigh the risks of addiction, abuse, and misuse, the Food and Drug Administration (FDA) has required a Risk Evaluation and Mitigation Strategy (REMS) for these products. Under the requirements of the REMS, drug companies with approved opioid analgesic products must make REMS-compliant education programs available to healthcare providers. Healthcare providers are strongly encouraged to do all of the following:

• Complete a REMS-compliant education program offered by an accredited provider of continuing education (CE) or another education program that includes all the elements of the FDA Education Blueprint for Health Care Providers Involved in the Management or Support of Patients with Pain.

• Discuss the safe use, serious risks, and proper storage and disposal of opioid analgesics with patients and/or their caregivers every time these medicines are prescribed. The Patient Counseling Guide (PCG) can be obtained at this link: www.fda.gov/OpioidAnalgesicREMSPCG.

• Emphasize to patients and their caregivers the importance of reading the Medication Guide that they will receive from their pharmacist every time an opioid analgesic is dispensed to them.

• Consider using other tools to improve patient, household, and community safety, such as patient-prescriber agreements that reinforce patient-prescriber responsibilities.

To obtain further information on the opioid analgesic REMS and for a list of accredited REMS CME/CE, call 1-800-503-0784, or log on to www.opioidanalgesicrems.com. The FDA Blueprint can be found at www.fda.gov/OpioidAnalgesicREMSBlueprint.

5.6 Risks of Concomitant Use or Discontinuation of Cytochrome P450 3A4 Inhibitors and Inducers

Concomitant use of hydrocodone bitartrate extended-release capsules with a CYP3A4 inhibitor, such as macrolide antibiotics (e.g., erythromycin), azole-antifungal agents (e.g., ketoconazole), and protease inhibitors (e.g., ritonavir), may increase plasma concentrations of hydrocodone and prolong opioid adverse reactions, which may cause potentially fatal respiratory depression [see Warnings and Precautions (5.2)], particularly when an inhibitor is added after a stable dose of hydrocodone bitartrate extended-release capsules is achieved. Similarly, discontinuation of a CYP3A4 inducer, such as rifampin, carbamazepine, and phenytoin, in hydrocodone bitartrate extended-release capsule-treated patients may increase hydrocodone plasma concentrations and prolong opioid adverse reactions. When using hydrocodone bitartrate extended-release capsules with CYP3A4 inhibitors or discontinuing CYP3A4 inducers in hydrocodone bitartrate extended-release capsule-treated patients, evaluate patients at frequent intervals and consider dosage reduction of hydrocodone bitartrate extended-release capsules until stable drug effects are achieved [see Drug Interactions (7)].

Concomitant use of hydrocodone bitartrate extended-release capsules with CYP3A4 inducers or discontinuation of an CYP3A4 inhibitor could decrease hydrocodone plasma concentrations, decrease opioid efficacy or, possibly, lead to a withdrawal syndrome in a patient who had developed physical dependence to hydrocodone. When using hydrocodone bitartrate extended-release capsules with CYP3A4 inducers or discontinuing CYP3A4 inhibitors, monitor patients closely at frequent intervals and consider increasing the opioid dosage if needed to maintain adequate analgesia or if symptoms of opioid withdrawal occur [see Drug Interactions (7)].

5.7 Opioid Induced Hyperalgesia and Allodynia

Opioid-Induced Hyperalgesia (OIH) occurs when an opioid analgesic paradoxically causes an increase in pain, or an increase in sensitivity to pain. This condition differs from tolerance, which is the need for increasing doses of opioids to maintain a defined effect [see Dependence (9.3)]. Symptoms of OIH include (but may not be limited to) increased levels of pain upon opioid dosage increase, decreased levels of pain upon opioid dosage decrease, or pain from ordinarily non-painful stimuli (allodynia). These symptoms may suggest OIH only if there is no evidence of underlying disease progression, opioid tolerance, opioid withdrawal, or addictive behavior.

Cases of OIH have been reported, both with short-term and longer-term use of opioid analgesics. Though the mechanism of OIH is not fully understood, multiple biochemical pathways have been implicated. Medical literature suggests a strong biologic plausibility between opioid analgesics and OIH and allodynia. If a patient is suspected to be experiencing OIH, carefully consider appropriately decreasing the dose of the current opioid analgesic or opioid rotation (safely switching the patient to a different opioid moiety) [see Dosage and Administration (2.6), Warnings and Precautions (5.14)].

5.8 Life-Threatening Respiratory Depression in Patients with Chronic Pulmonary Disease or in Elderly, Cachectic, or Debilitated Patients

The use of hydrocodone bitartrate extended-release capsules in patients with acute or severe bronchial asthma in an unmonitored setting or in the absence of resuscitative equipment is contraindicated.

Patients with Chronic Pulmonary Disease: Hydrocodone bitartrate extended-release capsule-treated patients with significant chronic obstructive pulmonary disease or cor pulmonale, and those with a substantially decreased respiratory reserve, hypoxia, hypercapnia, or pre-existing respiratory depression are at increased risk of decreased respiratory drive including apnea, even at recommended dosages of hydrocodone bitartrate extended-release capsules.

Elderly, Cachectic, or Debilitated Patients: Life-threatening respiratory depression is more likely to occur in elderly, cachectic, or debilitated patients because they may have altered pharmacokinetics or altered clearance compared to younger, healthier patients.

Regularly evaluate patients, particularly when initiating and titrating hydrocodone bitartrate extended-release capsules and when hydrocodone bitartrate extended-release capsules are given concomitantly with other drugs that depress respiration [see Warnings and Precautions (5), Drug Interactions (7)]. Alternatively, consider the use of non-opioid analgesics in these patients.

5.9 Adrenal Insufficiency

Cases of adrenal insufficiency have been reported with opioid use, more often following greater than one month of use. Presentation of adrenal insufficiency may include non-specific symptoms and signs including nausea, vomiting, anorexia, fatigue, weakness, dizziness, and low blood pressure. If adrenal insufficiency is suspected, confirm diagnosis with diagnostic testing as soon as possible. If adrenal insufficiency is diagnosed, treat with physiologic replacement doses of corticosteroids. Wean the patient off of the opioid to allow adrenal function to recover and continue corticosteroid treatment until adrenal function recovers. Other opioids may be tried as some cases reported use of a different opioid without recurrence of adrenal insufficiency. The information available does not identify any particular opioid as being more likely to be associated with adrenal insufficiency.

5.10 Severe Hypotension

Hydrocodone bitartrate extended-release capsules may cause severe hypotension including orthostatic hypotension and syncope in ambulatory patients. There is an added risk in patients whose ability to maintain blood pressure has already been compromised by a reduced blood volume, or after concurrent administration of certain CNS depressant drugs (e.g., phenothiazines or general anesthetics) [see Drug Interactions (7)]. Regularly evaluate these patients for signs of hypotension after initiating or titrating the dosage of hydrocodone bitartrate extended-release capsules. In patients with circulatory shock, hydrocodone bitartrate extended-release capsules may cause vasodilation that can further reduce cardiac output and blood pressure. Avoid the use of hydrocodone bitartrate extended-release capsules in patients with circulatory shock.

5.11 Risks of Use in Patients with Increased Intracranial Pressure, Brain Tumors, Head Injury, or Impaired Consciousness

In patients who may be susceptible to the intracranial effects of CO2 retention (e.g., those with evidence of increased intracranial pressure or brain tumors), hydrocodone bitartrate extended-release capsules may reduce respiratory drive, and the resultant CO2 retention can further increase intracranial pressure. Monitor such patients for signs of sedation and respiratory depression, particularly when initiating therapy with hydrocodone bitartrate extended-release capsules.

Opioids may also obscure the clinical course in a patient with a head injury. Avoid the use of hydrocodone bitartrate extended-release capsules in patients with impaired consciousness or coma.

5.12 Risks of Use in Patients with Gastrointestinal Conditions

Hydrocodone bitartrate extended-release capsules are contraindicated in patients with known or suspected gastrointestinal obstruction, including paralytic ileus. Hydrocodone in hydrocodone bitartrate extended-release capsules may cause spasm of the sphincter of Oddi. Opioids may cause increases in serum amylase. Regularly evaluate patients with biliary tract disease, including acute pancreatitis, for worsening of symptoms.

5.13 Increased Risk of Seizures in Patients with Seizure Disorders

The hydrocodone in hydrocodone bitartrate extended-release capsules may increase the frequency of seizures in patients with seizure disorders, and may increase the risk occurring in other clinical settings associated with seizures. Regularly evaluate patients with a history of seizure disorders for worsened seizure control during hydrocodone bitartrate extended-release capsules therapy.

5.14 Withdrawal

Do not abruptly discontinue hydrocodone bitartrate extended-release capsules in a patient physically dependent on opioids. When discontinuing hydrocodone bitartrate extended-release capsules in a physically dependent patient, gradually taper the dosage. Rapid tapering of hydrocodone in a patient physically dependent on opioids may lead to a withdrawal syndrome and return of pain [see Dosage and Administration (2.6), Drug Abuse and Dependence (9.3)].

Additionally, avoid the use of mixed agonist/antagonist (e.g., pentazocine, nalbuphine, and butorphanol) or partial agonist (e.g., buprenorphine) analgesics in patients who are receiving a full opioid agonist analgesic, including hydrocodone bitartrate extended-release capsules. In these patients, mixed agonist/antagonist and partial agonist analgesics may reduce the analgesic effect and/or may precipitate withdrawal symptoms [see Drug Interactions (7)].

5.15 Risks of Driving and Operating Machinery

Hydrocodone bitartrate extended-release capsules may impair the mental and physical abilities needed to perform potentially hazardous activities such as driving a car or operating machinery. Warn patients not to drive or operate dangerous machinery unless they are tolerant to the effects of hydrocodone bitartrate extended-release capsules and know how they will react to the medication [see Clinical Pharmacology (12.3), Patient Counseling Information (17)].

6 ADVERSE REACTIONS

The following serious adverse reactions are discussed elsewhere in the labeling:

- Addiction, Abuse, and Misuse [see Warnings and Precautions (5.1)]
- Life-Threatening Respiratory Depression [see Warnings and Precautions (5.2)]
- Risks from Concomitant Use with Benzodiazepines and Other CNS Depressants [see Warnings and Precautions (5.3)]
- Neonatal Opioid Withdrawal Syndrome [see Warnings and Precautions (5.4)]
- Opioid-Induced Hyperalgesia and Allodynia [see Warnings and Precautions (5.7)]
- Adrenal Insufficiency [see Warnings and Precautions (5.9)]
- Severe Hypotension [see Warnings and Precautions (5.10)]
- Gastrointestinal Adverse Reactions [see Warnings and Precautions (5.12)]
- Seizures [see Warnings and Precautions (5.13)]
- Withdrawal [see Warnings and Precautions (5.14)]

6.1 Clinical Trial Experience

Because clinical trials are conducted under widely varying conditions, adverse reaction rates observed in the clinical trials of a drug cannot be directly compared to rates in the clinical trials of another drug and may not reflect the rates observed in clinical practice.

The safety of hydrocodone bitartrate extended-release capsules was evaluated in a total of 1,148 subjects in Phase 3 clinical trials.

Table 2 lists the most frequently occurring adverse reactions occurring at a greater frequency than placebo from the placebo-controlled trial in subjects with moderate-to-severe chronic lower back pain.

Table 2. Treatment-Emergent Adverse Events in ≥2% of Subjects During the Open-Label Titration Period and/or the Double-Blind Treatment Period, by Preferred Term — Number (%) of Treated Subjects (Placebo-Controlled Study in Opioid-Experienced Subjects with Moderate-to-Severe Chronic Lower Back Pain)
 | Open-Label Titration Period | Double-Blind Treatment Period
 | Hydrocodone Bitartrate Extended-Release Capsules | Hydrocodone Bitartrate Extended-Release Capsules | Placebo
Preferred Term | (N = 510) | (n = 151) | (n = 151)
Constipation | 56 (11%) | 12 (8%) | 0 (0%)
Nausea | 50 (10%) | 11 (7%) | 5 (3%)
Somnolence | 24 (5%) | 1 (1%) | 0 (0%)
Fatigue | 21 (4%) | 1 (1%) | 2 (1%)
Headache | 19 (4%) | 0 (0%) | 2 (1%)
Dizziness | 17 (3%) | 3 (2%) | 1 (1%)
Dry mouth | 16 (3%) | 0 (0%) | 0 (0%)
Vomiting | 14 (3%) | 7 (5%) | 1 (1%)
Pruritus | 13 (3%) | 0 (0%) | 0 (0%)
Abdominal pain | 8 (2%) | 4 (3%) | 0 (0%)
Edema peripheral | 7 (1%) | 4 (3%) | 0 (0%)
Upper respiratory tract infection | 7 (1%) | 5 (3%) | 1 (1%)
Muscle spasms | 6 (1%) | 4 (3%) | 2 (1%)
Urinary tract infection | 4 (1%) | 8 (5%) | 3 (2%)
Back pain | 4 (1%) | 6 (4%) | 5 (3%)
Tremor | 1 (0%) | 4 (3%) | 1 (1%)

The common (≥1% to <10%) adverse drug reactions reported at least once by subjects treated with hydrocodone bitartrate extended-release capsules in the Phase 3 clinical trials and not represented in Table 2 were:

Gastrointestinal Disorders: abdominal discomfort, abdominal pain, gastroesophageal reflux disease

General Disorders and Administration Site Conditions: non-cardiac chest pain, pain, peripheral edema, pyrexia

Injury, Poisoning and Procedural Complications: contusion, fall, foot fracture, joint injury, joint sprain, muscle strain, skin laceration

Investigations: increased blood cholesterol, increased gamma-glutamyltransferase

Metabolism and Nutrition Disorders: dehydration, hypokalemia

Musculoskeletal and Connective Tissue Disorders: arthralgia, musculoskeletal pain, myalgia, neck pain, osteoarthritis, pain in extremity

Nervous System Disorders: lethargy, migraine, paresthesia

Psychiatric Disorders: anxiety, depression, insomnia

Respiratory, Thoracic, and Mediastinal Disorders: cough, dyspnea

Skin and Subcutaneous Tissue Disorders: hyperhidrosis, night sweats, rash

Vascular Disorders: hot flush

6.2 Postmarketing Experience

The following adverse reactions have been identified during post approval use of hydrocodone. Because these reactions are reported voluntarily from a population of uncertain size, it is not always possible to reliably estimate their frequency or establish a causal relationship to drug exposure.

Serotonin syndrome: Cases of serotonin syndrome, a potentially life-threatening condition, have been reported during concomitant use of opioids with serotonergic drugs.

Adrenal insufficiency: Cases of adrenal insufficiency have been reported with opioid use, more often following greater than one month of use.

Anaphylaxis: Anaphylaxis has been reported with ingredients contained in hydrocodone bitartrate extended-release capsules.

Androgen deficiency: Cases of androgen deficiency have occurred with use of opioids for an extended period of time [see Clinical Pharmacology (12.2)].

Hyperalgesia and Allodynia: Cases of hyperalgesia and allodynia have been reported with opioid therapy of any duration [see Warnings and Precautions (5.7)].

Hypoglycemia: Cases of hypoglycemia have been reported in patients taking opioids. Most reports were in patients with at least one predisposing risk factor (e.g., diabetes).

7 DRUG INTERACTIONS

Alcohol
Clinical Impact: | Concomitant use of alcohol with hydrocodone bitartrate extended-release capsules can result in an increase of hydrocodone plasma levels and potentially fatal overdose of hydrocodone.
Intervention: | Instruct patients not to consume alcoholic beverages or use prescription or non-prescription products containing alcohol while on hydrocodone bitartrate extended-release capsules therapy [see Clinical Pharmacology (12.3)].
Inhibitors of CYP3A4 and CYP2D6
Clinical Impact: | The concomitant use of hydrocodone bitartrate extended-release capsules and CYP3A4 inhibitors can increase the plasma concentration of hydrocodone, resulting in increased or prolonged opioid effects. These effects could be more pronounced with concomitant use of hydrocodone bitartrate extended-release capsules and CYP2D6 and CYP3A4 inhibitors, particularly when an inhibitor is added after a stable dose of hydrocodone bitartrate extended-release capsules is achieved [see Warnings and Precautions (5.6)]. After stopping a CYP3A4 inhibitor, as the effects of the inhibitor decline, the hydrocodone plasma concentration will decrease [see Clinical Pharmacology (12.3)], resulting in decreased opioid efficacy or a withdrawal syndrome in patients who had developed physical dependence to hydrocodone.
Intervention: | If concomitant use is necessary, consider dosage reduction of hydrocodone bitartrate extended-release capsules until stable drug effects are achieved. Evaluate patients at frequent intervals for respiratory depression and sedation. If a CYP3A4 inhibitor is discontinued, consider increasing the hydrocodone bitartrate extended-release capsules dosage until stable drug effects are achieved. Evaluate for signs of opioid withdrawal.
Examples: | Macrolide antibiotics (e.g., erythromycin), azole-antifungal agents (e.g. ketoconazole), protease inhibitors (e.g., ritonavir)
CYP3A4 Inducers
Clinical Impact: | The concomitant use of hydrocodone bitartrate extended-release capsules and CYP3A4 inducers can decrease the plasma concentration of hydrocodone [see Clinical Pharmacology (12.3)], resulting in decreased efficacy or onset of a withdrawal syndrome in patients who have developed physical dependence to hydrocodone [see Warnings and Precautions (5.6)]. After stopping a CYP3A4 inducer, as the effects of the inducer decline, the hydrocodone plasma concentration will increase [see Clinical Pharmacology (12.3)], which could increase or prolong both the therapeutic effects and adverse reactions, and may cause serious respiratory depression.
Intervention: | If concomitant use is necessary, consider increasing the hydrocodone bitartrate extended-release capsules dosage until stable drug effects are achieved. Evaluate for signs of opioid withdrawal. If a CYP3A4 inducer is discontinued, consider hydrocodone bitartrate extended-release capsules dosage reduction and evaluate patients at frequent intervals for signs of respiratory depression and sedation.
Examples: | Rifampin, carbamazepine, phenytoin
Benzodiazepines and other Central Nervous System (CNS) Depressants
Clinical Impact: | Due to additive pharmacologic effect, the concomitant use of benzodiazepines or other CNS depressants including alcohol, can increase the risk of hypotension, respiratory depression, profound sedation, coma, and death.
Intervention: | Reserve concomitant prescribing of these drugs for use in patients for whom alternative treatment options are inadequate. Limit dosages and durations to the minimum required. Inform patients and caregivers of this potential interaction, educate them on the signs and symptoms of respiratory depression (including sedation) [see Warnings and Precautions (5.3)]. If concomitant use is warranted, consider prescribing naloxone for the emergency treatment of opioid overdose [see Dosage and Administration (2.2), Warnings and Precautions (5.1, 5.2, 5.3)].
Examples: | Benzodiazepines and other sedatives/hypnotics, anxiolytics, tranquilizers, muscle relaxants, general anesthetics, antipsychotics, other opioids, alcohol.
Serotonergic Drugs
Clinical Impact: | The concomitant use of opioids with other drugs that affect the serotonergic neurotransmitter system has resulted in serotonin syndrome.
Intervention: | If concomitant use is warranted, frequently evaluate the patient, particularly during treatment initiation and dose adjustment. Discontinue hydrocodone bitartrate extended-release capsules if serotonin syndrome is suspected.
Examples: | Selective serotonin reuptake inhibitors (SSRIs), serotonin and norepinephrine reuptake inhibitors (SNRIs), tricyclic antidepressants (TCAs), triptans, 5-HT3 receptor antagonists, drugs that affect the serotonin neurotransmitter system (e.g., mirtazapine, trazodone, tramadol), monoamine oxidase (MAO) inhibitors (those intended to treat psychiatric disorders and also others, such as linezolid and intravenous methylene blue).
Monoamine Oxidase Inhibitors (MAOIs)
Clinical Impact: | MAOI interactions with opioids may manifest as serotonin syndrome or opioid toxicity (e.g., respiratory depression, coma) [see Drug Interactions (7)].
Intervention: | The use of hydrocodone bitartrate extended-release capsules is not recommended for patients taking MAOIs or within 14 days of stopping such treatment.
Examples: | Phenelzine, tranylcypromine, linezolid
Mixed Agonist/Antagonist and Partial Agonist Opioid Analgesics
Clinical Impact: | May reduce the analgesic effect of hydrocodone bitartrate extended-release capsules and/or precipitate withdrawal symptoms.
Intervention: | Avoid concomitant use.
Examples: | butorphanol, nalbuphine, pentazocine, buprenorphine
Muscle Relaxants
Clinical Impact: | Hydrocodone may enhance the neuromuscular blocking action of skeletal muscle relaxants and produce an increased degree of respiratory depression.
Intervention: | Because respiratory depression may be greater than otherwise expected, decrease the dosage of hydrocodone bitartrate extended-release capsules and/or the muscle relaxant as necessary. Due to the risk of respiratory depression with concomitant use of muscle relaxants and opioids, consider prescribing naloxone for the emergency treatment of opioid overdose [see Dosage and Administration (2.2), Warnings and Precautions (5.2, 5.3)].
Diuretics
Clinical Impact: | Opioids can reduce the efficacy of diuretics by inducing the release of antidiuretic hormone.
Intervention: | Evaluate patients for signs of diminished diuresis and/or effects on blood pressure and increase the dosage of the diuretic as needed.
Anticholinergic Drugs
Clinical Impact: | The concomitant use of anticholinergic drugs may increase risk of urinary retention and/or severe constipation, which may lead to paralytic ileus.
Intervention: | Evaluate patients for signs of urinary retention or reduced gastric motility when hydrocodone bitartrate extended-release capsules are used concomitantly with anticholinergic drugs.

8 USE IN SPECIFIC POPULATIONS

8.1 Pregnancy

Risk Summary

Use of opioid analgesics for an extended period of time during pregnancy may cause neonatal opioid withdrawal syndrome [see Warnings and Precautions (5.4)]. There are no studies of hydrocodone bitartrate extended-release capsules use in pregnant women. Rats administered oral hydrocodone during gestation and lactation showed increases in stillborn pups and decreases in pup survival at doses equivalent to the human dose of 100 mg/day. Reduced nursing behavior and decreased body weights were observed at 2 times the human dose. Reduced fetal weights were observed in rabbits administered hydrocodone during the period of organogenesis at doses equivalent to 5 times the human dose of 100 mg/day. In this study, increases in the number of umbilical hernias, irregularly shaped bones, and delays in fetal skeletal maturation were observed at doses 15 times the human dose of 100 mg/day. No fetal malformations were observed in animal reproduction studies with oral administration of hydrocodone bitartrate during organogenesis in rats and rabbits at doses approximately 2 and 10 times a human dose of 100 mg/day, respectively [see Data]. Based on animal data, advise pregnant women of the potential risks to a fetus.

The estimated background risk of major birth defects and miscarriage for the indicated population is unknown. All pregnancies have a background risk of birth defect, loss, or other adverse outcomes. In the U.S. general population, the estimated background risk of major birth defects and miscarriage in clinically recognized pregnancies is 2% to 4% and 15% to 20%, respectively.

Clinical Considerations

Fetal/neonatal adverse reactions

Use of opioid analgesics for an extended period of time during pregnancy for medical or nonmedical purposes can result in physical dependence in the neonate and neonatal opioid withdrawal syndrome shortly after birth. Observe newborns for symptoms of neonatal opioid withdrawal syndrome, such as poor feeding, diarrhea, irritability, tremor, rigidity, and seizures, and manage accordingly [see Warnings and Precautions (5.4)].

Labor or Delivery

Opioids cross the placenta and may produce respiratory depression and psycho-physiologic effects in neonates. An opioid antagonist such as naloxone must be available for reversal of opioid induced respiratory depression in the neonate. Hydrocodone bitartrate extended-release capsules are not recommended for use in women during and immediately prior to labor, when shorter-acting analgesics or other analgesic techniques are more appropriate. Opioid analgesics, including hydrocodone bitartrate extended-release capsules, can prolong labor through actions which temporarily reduce the strength, duration and frequency of uterine contractions. However, this effect is not consistent and may be offset by an increased rate of cervical dilatation, which tends to shorten labor.

Data

Animal Data

Oral doses of hydrocodone bitartrate up to 25 mg/kg/day in rats and 50 mg/kg/day in rabbits, equivalent to 2 and 10 times an adult human dose of 100 mg/day, respectively on a mg/m^2 basis, did not result in any fetal malformations. Fetuses of rabbits administered oral doses of 75 mg/kg/day hydrocodone bitartrate (15 times an adult human dose of 100 mg/day on a mg/m^2 basis) during the period of organogenesis exhibited an increased number of malformations consisting of umbilical hernia, and irregularly shaped bones (ulna, femur, tibia and/or fibula). Maternal toxicity was evident at this dose (decreased body weight). In addition, oral hydrocodone bitartrate reduced fetal weights at doses greater than or equal to 25 mg/kg/day (equivalent to approximately 5 times an adult human dose of 100 mg/day on a mg/m^2 basis). Delays in fetal skeletal maturation (reduced ossification of hyoid bodies and xiphoid bones) were seen following dosing with 75 mg/kg/day (a dose equivalent to 15 times an adult human dose of 100 mg/day on a mg/m^2 basis).

Hydrocodone bitartrate administered orally to female rats at oral doses of 10 mg/kg/day and 25 mg/kg/day during gestation and lactation resulted in pups which were noted as cold to touch and caused a reduction in fetal viability (increases in the number of stillborn pups and/or pups dying postpartum). The doses causing these effects were equivalent to approximately 1 and 2.4 times an adult human dose of 100 mg/day, on a mg/m^2 basis. Nursing was reduced in pups of mothers administered 25 mg/kg/day which correlated with decreased body weight/body weight gain and food consumption in male pups. Minimal maternal toxicity was evident at 25 mg/kg (decreased body weight).

8.2 Lactation

Risk Summary

Hydrocodone is present in human milk. A published lactation study reports variable concentrations of hydrocodone and hydromorphone (an active metabolite) in breast milk with administration of immediate-release hydrocodone to nursing mothers in the early post-partum period. This lactation study did not assess breastfed infants for potential adverse drug reactions. Lactation studies have not been conducted with extended-release hydrocodone, including hydrocodone bitartrate extended-release capsules, and no information is available on the effects of the drug on the breastfed infant or the effects of the drug on milk production.

Because of the potential for serious adverse reactions, including excess sedation and respiratory depression in a breastfed infant, advise patients that breastfeeding is not recommended during treatment with hydrocodone bitartrate extended-release capsules.

Clinical Considerations

Monitor infants exposed to hydrocodone bitartrate through breast milk for excess sedation and respiratory depression. Withdrawal symptoms can occur in breastfed infants when maternal administration of an opioid analgesic is stopped, or when breastfeeding is stopped.

8.3 Females and Males of Reproductive Potential

Infertility

Use of opioids for an extended period of time may cause reduced fertility in females and males of reproductive potential. It is not known whether these effects on fertility are reversible.

In rat fertility studies, no effects on male fertility were observed with hydrocodone at doses equivalent to 10 times the human dose of 100 mg/day, however, decreases in the weight of male reproductive organs were observed in all treated groups at doses equivalent to 2.4 times the human dose of 100 mg/day and above. Reductions in female fertility indices were observed at doses of hydrocodone equivalent to 2 times the human dose of 100 mg/day and above. These changes are attributed to a hydrocodone-mediated decrease in prolactin levels in the rat. Unique to rodents, prolactin is required for normal estrous cycling and the effects on fertility observed in this study are most likely rodent-specific and not believed to be clinically relevant [see Nonclinical Toxicology (13)].

8.4 Pediatric Use

The safety and effectiveness of hydrocodone bitartrate extended-release capsules in pediatric patients below the age of 18 years have not been established.

8.5 Geriatric Use

Clinical studies of hydrocodone bitartrate extended-release capsules did not include sufficient numbers of subjects aged 65 and over to determine whether they respond differently from younger subjects. Elderly patients (aged 65 years or older) may have increased sensitivity to hydrocodone. In general, use caution when selecting a dosage for an elderly patient, usually starting at the low end of the dosing range, reflecting the greater frequency of decreased hepatic, renal, or cardiac function, and of the concomitant disease or other drug therapy.

Respiratory depression is the chief risk for elderly patients treated with opioids, and has occurred after large initial doses were administered to patients who were not opioid-tolerant or when opioids were co-administered with other agents that depress respiration. Titrate the dosage of hydrocodone bitartrate extended-release capsules slowly in geriatric patients and frequently reevaluate the patient for signs of central nervous system and respiratory depression [see Warnings and Precautions (5.8)].

Hydrocodone is known to be substantially excreted by the kidney, and the risk of adverse reactions to this drug may be greater in patients with impaired renal function. Because elderly patients are more likely to have decreased renal function, care should be taken in dose selection, and it may be useful to regularly evaluate renal function.

8.6 Hepatic Impairment

No adjustment in starting dose with hydrocodone bitartrate extended-release capsules is required in patients with mild or moderate hepatic impairment. Patients with severe hepatic impairment may have higher plasma concentrations than those with normal hepatic function [see Clinical Pharmacology (12.3)]. Therefore, a dosage reduction is recommended for patients with severe hepatic impairment [see Dosage and Administration (2.5)]. Regularly evaluate patients with severe hepatic impairment for respiratory depression, sedation, and hypotension [see Clinical Pharmacology (12.3)].

8.7 Renal Impairment

Patients with renal impairment have higher plasma concentrations than those with normal function. Use a low initial dose of hydrocodone bitartrate extended-release capsules in patients with renal impairment and regularly evaluate for respiratory depression, sedation, and hypotension [see Clinical Pharmacology (12.3)].

9 DRUG ABUSE AND DEPENDENCE

9.1 Controlled Substance

Hydrocodone bitartrate extended-release capsules contain hydrocodone bitartrate, a Schedule II controlled substance.

9.2 Abuse

Hydrocodone bitartrate extended-release capsules contain hydrocodone, a substance with high potential for misuse and abuse, which can lead to the development of substance use disorder, including addiction [see Warnings and Precautions (5.1)].

Misuse is the intentional use, for therapeutic purposes, of a drug by an individual in a way other than prescribed by a healthcare provider or for whom it was not prescribed.

Abuse is the intentional, non-therapeutic use of a drug, even once, for its desirable psychological or physiological effects.

Drug addiction is a cluster of behavioral, cognitive, and physiological phenomena that may include a strong desire to take the drug, difficulties in controlling drug use (e.g., continuing drug use despite harmful consequences, giving a higher priority to drug use than other activities and obligations), and possible tolerance or physical dependence.

Misuse and abuse of hydrocodone bitartrate extended-release capsules increases risk of overdose, which may lead to central nervous system and respiratory depression, hypotension, seizures, and death. The risk is increased with concurrent abuse of hydrocodone bitartrate extended-release capsules with alcohol and other CNS depressants. Abuse of and addiction to opioids in some individuals may not be accompanied by concurrent tolerance and symptoms of physical dependence. In addition, abuse of opioids can occur in the absence of addiction.

All patients treated with opioids require careful and frequent reevaluation for signs of misuse, abuse, and addiction, because use of opioid analgesic products carries the risk of addiction even under appropriate medical use. Patients at high risk of hydrocodone bitartrate extended-release capsules abuse include those with a history of prolonged use of any opioid, including products containing hydrocodone, those with a history of drug or alcohol abuse, or those who use hydrocodone bitartrate extended-release capsules in combination with other abused drugs.

"Drug-seeking" behavior is very common in persons with substance use disorders. Drug-seeking tactics include emergency calls or visits near the end of office hours, refusal to undergo appropriate examination, testing, or referral, repeated “loss” of prescriptions, tampering with prescriptions, and reluctance to provide prior medical records or contact information for other treating healthcare provider(s). “Doctor shopping” (visiting multiple prescribers to obtain additional prescriptions) is common among people who abuse drugs and people with substance use disorder. Preoccupation with achieving adequate pain relief can be appropriate behavior in a patient with inadequate pain control.

Hydrocodone bitartrate extended-release capsules, like other opioids, can be diverted for nonmedical use into illicit channels of distribution. Careful record-keeping of prescribing information, including quantity, frequency, and renewal requests, as required by state and federal law, is strongly advised.

Proper assessment of the patient, proper prescribing practices, periodic re-evaluation of therapy, and proper dispensing and storage are appropriate measures that help to limit abuse of opioid drugs.

Risks Specific to Abuse of Hydrocodone Bitartrate Extended-Release Capsules

Abuse of hydrocodone bitartrate extended-release capsules poses a risk of overdose and death. The risk is increased with concurrent use of hydrocodone bitartrate extended-release capsules with alcohol and/or other CNS depressants. Taking cut, broken, chewed, crushed, or dissolved hydrocodone bitartrate extended-release capsules enhances drug release and increases the risk of overdose and death.

Hydrocodone bitartrate extended-release capsules are approved for oral use only. With parenteral abuse the inactive ingredients can result in local tissue necrosis, infection, pulmonary granulomas, increased risk of endocarditis and valvular heart injury, embolism, and death.

Parenteral drug abuse is commonly associated with transmission of infectious diseases such as hepatitis and HIV.

9.3 Dependence

Both tolerance and physical dependence can develop during use of opioid therapy.

Tolerance is a physiological state characterized by a reduced response to a drug after repeated administration (i.e., a higher dose of a drug is required to produce the same effect that was once obtained at a lower dose).

Physical dependence is a state that develops as a result of a physiological adaptation in response to repeated drug use, manifested by withdrawal signs and symptoms after abrupt discontinuation or a significant dose reduction of a drug.

Withdrawal may be precipitated through the administration of drugs with opioid antagonist activity (e.g., naloxone), mixed agonist/antagonist analgesics (e.g., pentazocine, butorphanol, nalbuphine), or partial agonists (e.g., buprenorphine). Physical dependence may not occur to a clinically significant degree until after several days to weeks of continued use.

Do not abruptly discontinue hydrocodone bitartrate extended-release capsules in a patient physically dependent on opioids. Rapid tapering of hydrocodone bitartrate extended-release capsules in a patient physically dependent on opioids may lead to serious withdrawal symptoms, uncontrolled pain, and suicide. Rapid discontinuation has also been associated with attempts to find other sources of opioid analgesics, which may be confused with drug-seeking for abuse.

When discontinuing hydrocodone bitartrate extended-release capsules, gradually taper the dosage using a patient-specific plan that considers the following: the dose of hydrocodone bitartrate extended-release capsules the patient has been taking, the duration of treatment, and the physical and psychological attributes of the patient. To improve the likelihood of a successful taper and minimize withdrawal symptoms, it is important that the opioid tapering schedule is agreed upon by the patient. In patients taking opioids for an extended period of time at high doses, ensure that a multimodal approach to pain management, including mental health support (if needed), is in place prior to initiating an opioid analgesic taper [see Dosage and Administration (2.6), Warnings and Precautions (5.14)].

Infants born to mothers physically dependent on opioids will also be physically dependent and may exhibit respiratory difficulties and withdrawal signs [see Use in Specific Populations (8.1)].

10 OVERDOSAGE

Clinical Presentation

Acute overdosage with hydrocodone bitartrate extended-release capsules can be manifested by respiratory depression, somnolence progressing to stupor or coma, skeletal muscle flaccidity, cold and clammy skin, constricted pupils, and, in some cases, pulmonary edema, bradycardia, hypotension, hypoglycemia, partial or complete airway obstruction, atypical snoring, and death. Marked mydriasis rather than miosis may be seen with hypoxia in overdose situations [see Clinical Pharmacology (12.2)].

Treatment of Overdose

In case of overdose, priorities are the reestablishment of a patent and protected airway and institution of assisted or controlled ventilation, if needed. Employ other supportive measures (including oxygen and vasopressors) in the management of circulatory shock and pulmonary edema as indicated. Cardiac arrest or arrhythmias will require advanced life-support measures.

Opioid antagonists, such as naloxone, are specific antidotes to respiratory depression resulting from opioid overdosage. For clinically significant respiratory or circulatory depression secondary to hydrocodone overdose, administer an opioid antagonist.

Because the duration of reversal is expected to be less than the duration of action of hydrocodone in hydrocodone bitartrate extended-release capsules, carefully monitor the patient until spontaneous respiration is reliably reestablished. Hydrocodone bitartrate extended-release capsules will continue to release hydrocodone and add to the hydrocodone load for 24 to 48 hours or longer following ingestion necessitating prolonged monitoring. If the response to an opioid antagonist is suboptimal or only brief in nature, administer additional antagonist as directed by the product’s prescribing information.

In an individual physically dependent on opioids, administration of the recommended dose of the antagonist will precipitate an acute withdrawal syndrome. The severity of the withdrawal syndrome produced will depend on the degree of physical dependence and the dose of the antagonist administered. If a decision is made to treat serious respiratory depression in the physically dependent patient, administration of the antagonist should be initiated with care and by titration with smaller than usual doses of the antagonist.

11 DESCRIPTION

Hydrocodone bitartrate extended-release capsules are hard gelatin capsules for oral administration. Hydrocodone bitartrate is an opioid agonist and occurs as fine, white crystals, or as a crystalline powder.

The chemical name is 4,5(alpha)-epoxy-3-methoxy-17-methylmorphinan-6-one tartrate (1:1) hydrate (2:5) or morphinan-6-one, 4,5-epoxy-3-methoxy-17-methyl-, (5 alpha)-, [R (R*, R*)]-2,3-dihydroxybutanedioate (1:1), hydrate (2:5). It has the following structural formula:

Each hydrocodone bitartrate extended-release capsule contains either 10 mg, 15 mg, 20 mg, 30 mg, 40 mg, or 50 mg of hydrocodone bitartrate USP. All capsule strengths include the following inactive ingredients: ammonio methacrylate copolymer Type B, copovidone, gelatin, silicon dioxide, sodium lauryl sulfate, sugar spheres, and talc.

The capsule shells contain the following colorants: black iron oxide (50 mg capsule), D&C yellow #10 (all capsule strengths), FD&C blue #1 (10 mg, 15 mg, and 30 mg capsules), FD&C red #3 (15 mg and 30 mg capsules), FD&C red #40 (30 mg capsule), FD&C yellow #6 (all capsule strengths) and titanium dioxide (all capsule strengths).

The imprinting ink for all capsule strengths contains: black iron oxide, D&C yellow #10, FD&C blue #1, FD&C blue #2, FD&C red # 40, n-butyl alcohol, propylene glycol and shellac.

12 CLINICAL PHARMACOLOGY

12.1 Mechanism of Action

Hydrocodone is a full opioid agonist with relative selectivity for the mu-opioid receptor, although it can interact with other opioid receptors at higher doses. The principal therapeutic action of hydrocodone is analgesia. Like all full opioid agonists, there is no ceiling effect for analgesia with hydrocodone. Clinically, dosage is titrated to provide adequate analgesia and may be limited by adverse reactions, including respiratory and CNS depression.

The precise mechanism of the analgesic action is unknown. However, specific CNS opioid receptors for endogenous compounds with opioid-like activity have been identified throughout the brain and spinal cord and are thought to play a role in the analgesic effects of this drug.

12.2 Pharmacodynamics

Effects on the Central Nervous System

Hydrocodone produces respiratory depression by direct action on brain stem respiratory centers. The respiratory depression involves a reduction in the responsiveness of the brainstem respiratory centers to both increases in carbon dioxide tension and electrical stimulation. Hydrocodone causes miosis, even in total darkness. Pinpoint pupils are a sign of opioid overdose but are not pathognomonic (e.g., pontine lesions of hemorrhagic or ischemic origin may produce similar findings). Marked mydriasis rather than miosis may be seen with hypoxia in overdose situations [see Overdosage (10)].

Effects on the Gastrointestinal Tract and Other Smooth Muscle

Hydrocodone causes a reduction in motility associated with an increase in smooth muscle tone in the antrum of the stomach and duodenum. Digestion of food in the small intestine is delayed and propulsive contractions are decreased. Propulsive peristaltic waves in the colon are decreased, while tone is increased to the point of spasm, resulting in constipation. Other opioid-induced effects may include a reduction in gastric, in biliary and pancreatic secretions, spasm of sphincter of Oddi, and transient elevations in serum amylase.

Effects on the Cardiovascular System

Hydrocodone produces peripheral vasodilation, which may result in orthostatic hypotension or syncope. Manifestations of histamine release and/or peripheral vasodilation may include pruritus, flushing, red eyes, sweating, and/or orthostatic hypotension.

Effects on the Endocrine System

Opioids inhibit the secretion of adrenocorticotropic hormone (ACTH), cortisol, and luteinizing hormone (LH) in humans [see Adverse Reactions (6.2)]. They also stimulate prolactin, growth hormone (GH) secretion, and pancreatic secretion of insulin and glucagon.

Use of opioids for an extended period of time may influence the hypothalamic-pituitary-gonadal axis, leading to androgen deficiency that may manifest as low libido, impotence, erectile dysfunction, amenorrhea, or infertility. The causal role of opioids in the clinical syndrome of hypogonadism is unknown because the various medical, physical, lifestyle, and psychological stressors that may influence gonadal hormone levels have not been adequately controlled for in studies conducted to date [see Adverse Reactions (6.2)].

Effects on the Immune System

In vitro and animal studies indicate that opioids have a variety of effects on immune functions, depending on the context in which they are used. The clinical significance of these findings is unknown. Overall, the effects of opioids appear to be modestly immunosuppressive.

Concentration—Efficacy Relationships

The minimum effective analgesic concentration will vary widely among patients, especially among patients who have been previously treated with opioid agonists. The minimum effective analgesic concentration of hydrocodone for any individual patient may increase over time due to an increase in pain, the development of a new pain syndrome, and/or the development of analgesic tolerance [see Dosage and Administration (2.1, 2.4)].

Concentration—Adverse Experience Relationships

There is a relationship between increasing hydrocodone plasma concentration and increasing frequency of adverse experiences such as nausea, vomiting, CNS effects, and respiratory depression. In opioid-tolerant patients, the situation may be altered by the development of tolerance to opioid-related adverse reactions [see Dosage and Administration (2.1, 2.3, 2.4)].

12.3 Pharmacokinetics

Absorption

As compared to immediate-release hydrocodone combination products, hydrocodone bitartrate extended-release capsules at similar daily doses results in similar overall exposure but with lower maximum concentrations. The half-life is also longer due to the prolonged duration of absorption. Based on the half-life of hydrocodone, steady-state should be obtained after 3 days of dosing. Following 7 days of dosing, AUC and Cmax increase approximately two-fold as compared to the first day of dosing. The pharmacokinetics of hydrocodone bitartrate extended-release capsules have been shown to be independent of dose up to a dose of 50 mg.

Hydrocodone bitartrate extended-release capsules exhibit peak plasma concentrations approximately 5 hours after dose administration.

Food Effects

Food has no significant effect on the extent of absorption of hydrocodone from hydrocodone bitartrate extended-release capsules. Although there was no evidence of dose dumping associated with this formulation under fasted and fed conditions, peak plasma concentration of hydrocodone increased by 27% when a hydrocodone bitartrate extended-release 20 mg capsule was administered with a high-fat meal.

Distribution

Although the extent of protein binding of hydrocodone in human plasma has not been definitively determined, structural similarities to related opioid analgesics suggest that hydrocodone is not extensively protein bound. As most agents in the 5-ring morphinan group of semi-synthetic opioids bind plasma protein to a similar degree (range 19% [hydromorphone] to 45% [oxycodone]), hydrocodone is expected to fall within this range.

Elimination

Metabolism

Hydrocodone exhibits a complex pattern of metabolism, including N-demethylation, O-demethylation, and 6-keto reduction to the corresponding 6-α-and 6-β-hydroxy metabolites. CYP3A4 mediated N-demethylation to norhydrocodone is the primary metabolic pathway of hydrocodone with a lower contribution from CYP2D6 mediated O-demethylation to hydromorphone. Hydromorphone is formed from the O-demethylation of hydrocodone and may contribute to the total analgesic effect of hydrocodone. Therefore, the formation of these and related metabolites can, in theory, be affected by other drugs [see Drug Interactions (7)]. Published in vitro studies have shown that N-demethylation of hydrocodone to form norhydrocodone can be attributed to CYP3A4 while O-demethylation of hydrocodone to hydromorphone is predominantly catalyzed by CYP2D6 and to a lesser extent by an unknown low affinity CYP enzyme.

Excretion

Hydrocodone and its metabolites are eliminated primarily in the kidneys, with a mean apparent plasma half-life after hydrocodone bitartrate extended-release capsules administration of approximately 8 hours.

Special Populations

Age: Geriatric Patients

No significant pharmacokinetic differences by age were observed based on population pharmacokinetic analysis.

Sex: No significant pharmacokinetic differences by sex were observed based on population pharmacokinetic analysis.

Hepatic Impairment

After a single dose of 20 mg hydrocodone bitartrate extended-release capsules in 20 patients with mild to moderate hepatic impairment based on Child-Pugh classifications, mean hydrocodone Cmax values were 25 ± 5 ng/mL, 24 ± 5 ng/mL, and 22 ± 3.3 ng/mL for moderate and mild impairment, and normal subjects, respectively. Mean hydrocodone AUC values were 509 ± 157 ng∙h/mL, 440 ± 124 ng∙h/mL, and 391 ± 74 ng∙h/mL for moderate and mild impairment, and normal subjects, respectively. Hydrocodone Cmax values were 8% to 10% higher in patients with mild or moderate hepatic impairment, respectively, while AUC values were 10% and 26% higher in patients with mild and moderate hepatic impairment, respectively. Severely impaired subjects were not studied [see Use in Specific Populations (8.6)].

Renal Impairment

After a single dose of 20 mg hydrocodone bitartrate extended-release capsules in 28 patients with mild, moderate, or severe renal impairment based on Cockcroft-Gault criteria, mean hydrocodone Cmax values were 26 ± 6.0 ng/mL, 28 ± 7.5 ng/mL, 21 ± 5.1 ng/mL and 19 ± 4.4 ng/mL for severe, moderate, mild renal impairment, and normal subjects, respectively. Mean hydrocodone AUC values were 487 ± 123 ng∙h/mL, 547 ± 184 ng∙h/mL, 391 ± 122 ng∙h/mL and 343 ± 105 ng∙h/mL for severe, moderate, mild renal impairment, and normal subjects, respectively. Hydrocodone Cmax values were 15%, 48%, and 41% higher and AUC values were 15%, 57% and 44% higher in patients with mild, moderate, and severe renal impairment, respectively [see Use in Specific Populations (8.7)].

Drug Interaction Studies

Interactions with Alcohol

The rate of absorption of hydrocodone bitartrate extended-release capsules 50 mg was affected by co-administration with 40% alcohol in the fasted state, as exhibited by an increase in peak hydrocodone concentrations (on average 2.4-fold increase with maximum increase of 3.9-fold in one subject) and a decrease in the time to peak concentrations. The extent of absorption was increased on average 1.2-fold with maximum increase of 1.7-fold in one subject with 40% alcohol [see Warnings and Precautions (5.3)].

Cytochrome P450 Enzymes

While comprehensive PK drug-drug interaction studies (other than alcohol) have not been performed in humans receiving hydrocodone, published in vitro and human PK studies indicate that conversion of hydrocodone to its primary metabolite, norhydrocodone and lesser metabolite, hydromorphone, is mediated by the cytochrome P450 enzyme system. N-demethylation of hydrocodone to form norhydrocodone is attributed to CYP3A4 and O-demethylation of hydrocodone to hydromorphone is predominantly catalyzed by CYP2D6 and to a lesser extent by an unknown low affinity CYP enzyme.

CYP3A4 Inhibitors and Inducers

An increase in CYP3A4 activity by initiation of CYP3A4 inhibiting drugs or discontinuation of CYP3A4 inducing drugs could alter the metabolic profile of hydrocodone causing a slowing of hydrocodone clearance, and lead to elevated hydrocodone concentrations and effects, which could be more pronounced with concomitant use of cytochrome P450 CYP3A4 inhibitors. Initiation of a CYP3A4 inducing drug can lower hydrocodone plasma levels and may induce an opioid-withdrawal syndrome [see Warnings and Precautions (5.6) and Drug Interactions (7)].

13 NONCLINICAL TOXICOLOGY

13.1 Carcinogenesis, Mutagenesis, Impairment of Fertility

Carcinogenesis

Hydrocodone was evaluated for carcinogenic potential in rats and mice. In a two-year bioassay in rats, doses up to 30 mg/kg in males and 100 mg/kg in females were administered orally and no treatment-related neoplasms were observed (exposure is equivalent to 0.1 times and 0.6 times for males and females, respectively, the human hydrocodone dose of 100 mg/day based on AUC exposure comparisons). In a two-year bioassay in mice, doses up to 100 mg/kg in males and females were administered orally and no treatment-related neoplasms were observed (exposure is equivalent to 0.8 times and 1.5 times, respectively, the human hydrocodone dose of 100 mg/day based on AUC exposure comparisons).

Mutagenesis

Hydrocodone bitartrate was genotoxic in an in vitro chromosomal aberration assay in the presence of metabolic activation. No evidence of clastogenicity was observed in this assay in the absence of metabolic activation. No evidence of DNA damage was found in an in vivo comet assay in mouse liver. There was no evidence of genotoxic potential in an in vitro bacterial reverse mutation assay (Salmonella typhimurium and Escherichia coli) or in an assay for chromosomal aberrations (in vivo mouse bone marrow micronucleus assay).

Impairment of Fertility

In a fertility study, rats were administered once daily by oral gavage the vehicle or hydrocodone bitartrate at doses of 25 mg/kg/day, 75 mg/kg/day, and 100 mg/kg/day (equivalent to approximately 2, 7, and 10 times an adult human dose of 100 mg/day, on a mg/m^2 basis). Male and female rats were dosed before cohabitation (up to 28 days), during the cohabitation and until gestation day 7 (females) or necropsy (males; 2 to 3 weeks post-cohabitation). Hydrocodone bitartrate did not affect reproductive function in males, although the weights of male reproductive organs were decreased at all doses. Doses of 25 mg/kg/day and greater in females reduced the rate at which females became pregnant which correlated with suppression of estrous cyclicity, thought to be due to increases in prolactin. In hydrocodone bitartrate-treated rats that became pregnant, at 25 mg/kg early embryonic development was unaffected (approximately 2 times the adult human daily dose of 100 mg/day on a mg/m^2 basis). In rats, prolactin plays a unique role in the estrous cycle and the clinical relevance of the female rat reproductive findings is uncertain.

14 CLINICAL STUDIES

The efficacy and safety of hydrocodone bitartrate extended-release capsules have been evaluated in a randomized double-blind, placebo-controlled, multi-center clinical trial in opioid-experienced subjects with moderate to severe chronic low back pain.

Placebo-Controlled Study in Opioid-Experienced Subjects with Moderate to Severe Chronic Lower Back Pain

A total of 510 subjects currently on chronic opioid therapy entered an open-label conversion and titration phase (up to 6 weeks) with hydrocodone bitartrate extended-release capsules dosed every 12 hours at an approximated equianalgesic dose of their pre-study opioid medication. For inadequately controlled pain, hydrocodone bitartrate extended-release capsules was increased by 10 mg per 12-hour dose, once every 3 to 7 days until a stabilized dose was identified, or a maximum dosage of 100 mg every 12 hours. There were 302 subjects (59%) randomized at a ratio of 1:1 into a 12-week double-blind treatment phase with their fixed stabilized dose of hydrocodone bitartrate extended-release capsules (40 mg to 200 mg daily taken as 20 mg to 100 mg, every 12 hours) or a matching placebo. Subjects randomized to placebo were given a blinded taper of hydrocodone bitartrate extended-release capsules according to a pre-specified tapering schedule. During the treatment phase, subjects were allowed to use rescue medication (hydrocodone 5 mg/500 mg acetaminophen) up to 2 doses (2 tablets) per day. There were 124 treated subjects (82%) that completed the 12-week treatment with hydrocodone bitartrate extended-release capsules and 59 subjects (39%) with placebo.

Hydrocodone bitartrate extended-release capsules provided greater analgesia compared to placebo. There was a significant difference in the mean changes from Baseline to Week 12 in average weekly pain intensity Numeric Rating Scale (NRS) scores between the two groups.

The percentage of subjects in each group who demonstrated improvement in their NRS pain score at End-of-Study, as compared to Screening is shown in the figure below. The figure is cumulative, so subjects whose change from Screening is, for example, 30% are also included at every level of improvement below 30%. Subjects who did not complete the study were classified as non-responders. Treatment with hydrocodone bitartrate extended-release capsules produced a greater number of responders, defined as subjects with at least a 30% improvement, as compared to placebo (67.5% vs. 31.1%).

16 HOW SUPPLIED/STORAGE AND HANDLING

Hydrocodone bitartrate extended-release capsules are supplied in bottles with child-resistant closures as follows:

Strength | Capsule Color(s) | Capsule Text | NDC Number
10 mg | Light blue cap and yellow body | "ALV" printed on the cap and "409" printed on the body in grey ink | 47781-409-60 60 Count Bottle
15 mg | Light lavender cap and yellow body | "ALV" printed on the cap and "410" printed on the body in grey ink | 47781-410-60 60 Count Bottle
20 mg | White cap and yellow body | "ALV" printed on the cap and "411" printed on the body in grey ink | 47781-411-60 60 Count Bottle
30 mg | Light pink cap and yellow body | "ALV" printed on the cap and "412" printed on the body in grey ink | 47781-412-60 60 Count Bottle
40 mg | Yellow cap and yellow body | "ALV" printed on the cap and "413" printed on the body in grey ink | 47781-413-60 60 Count Bottle
50 mg | Light grey cap and yellow body | "ALV" printed on the cap and "414" printed on the body in grey ink | 47781-414-60 60 Count Bottle

Hydrocodone bitartrate extended-release capsules contain hydrocodone bitartrate which is a controlled substance and is controlled under Schedule II of the Controlled Substances Act. Hydrocodone, like all opioids, is liable to diversion and misuse and should be handled accordingly. Patients and their families should be instructed to dispose of any hydrocodone bitartrate extended-release capsules that are no longer needed.

Hydrocodone bitartrate extended-release capsules may be targeted for theft and diversion. Healthcare professionals should contact their State Medical Board, State Board of Pharmacy, or State Control Board for information on how to detect or prevent diversion of this product.

Healthcare professionals should advise patients to store hydrocodone bitartrate extended-release capsules in a secure place, preferably locked and out of the reach of children and other non-caregivers.

Store at 25°C (77°F); excursions permitted to 15° to 30°C (59° to 86°F) [see USP Controlled Room Temperature].

Dispense in tight container as defined in the USP, with a child-resistant closure.

Advise patients to dispose of any unused capsules from a prescription as soon as they are no longer needed in accordance with local State guidelines and/or regulations [see Patient Counseling Information (17)].

17 PATIENT COUNSELING INFORMATION

Advise the patient to read the FDA approved patient labeling (Medication Guide).

Storage and Disposal

Because of the risks associated with accidental ingestion, misuse, and abuse, advise patients to store hydrocodone bitartrate extended-release capsules securely, out of sight and reach of children, and in a location not accessible by others, including visitors to the home. Inform patients that leaving hydrocodone bitartrate extended-release capsules unsecured can pose a deadly risk to others in the home [see Warnings and Precautions (5.1), Drug Abuse and Dependence (9.2)].

Advise patients and caregivers that when medicines are no longer needed, they should be disposed of promptly. Expired, unwanted, or unused hydrocodone bitartrate extended-release capsules should be disposed of by flushing the unused medication down the toilet if a drug take-back option is not readily available. Inform patients that they can visit www.fda.gov/drugdisposal for a complete list of medicines recommended for disposal by flushing, as well as additional information on disposal of unused medicines.

Addiction, Abuse, and Misuse

Inform patients that the use of hydrocodone bitartrate extended-release capsules, even when taken as recommended, can result in addiction, abuse, and misuse, which can lead to overdose or death [see Warnings and Precautions (5.1)]. Instruct patients not to share hydrocodone bitartrate extended-release capsules with others and to take steps to protect hydrocodone bitartrate extended-release capsules from theft or misuse.

Life-Threatening Respiratory Depression

Inform patients of the risk of life-threatening respiratory depression, including information that the risk is greatest when starting hydrocodone bitartrate extended-release capsules or when the dosage is increased, and that it can occur even at recommended dosages.

Educate patients and caregivers on how to recognize respiratory depression and emphasize the importance of calling 911 or getting emergency medical help right away in the event of a known or suspected overdose [see Warnings and Precautions (5.2)].

Accidental Ingestion

Inform patients that accidental ingestion, especially by children, may result in respiratory depression or death [see Warnings and Precautions (5.2)].

Interactions with Benzodiazepines and Other CNS Depressants

Inform patients and caregivers that potentially fatal additive effects may occur if hydrocodone bitartrate extended-release capsules are used with benzodiazepines or other CNS depressants, including alcohol, and not to use these concomitantly unless supervised by a health care provider. Instruct patients not to consume alcoholic beverages, as well as prescription and over-the-counter products that contain alcohol, during treatment with hydrocodone bitartrate extended-release capsules [see Warnings and Precautions (5.3), Drug Interactions (7)].

Patient Access to Naloxone for the Emergency Treatment of Opioid Overdose

Discuss with the patient and caregiver the availability of naloxone for the emergency treatment of opioid overdose, both when initiating and renewing treatment with hydrocodone bitartrate extended-release capsules. Inform patients and caregivers about the various ways to obtain naloxone as permitted by individual state naloxone dispensing and prescribing requirements or guidelines (e.g., by prescription, directly from a pharmacist, or as part of a community-based program) [see Dosage and Administration (2.2), Warnings and Precautions (5.2)].

Educate patients and caregivers on how to recognize the signs and symptoms of an overdose.

Explain to patients and caregivers that naloxone’s effects are temporary, and that they must call 911 or get emergency medical help right away in all cases of known or suspected opioid overdose, even if naloxone is administered [see Overdosage (10)].

If naloxone is prescribed, also advise patients and caregivers:

- How to treat with naloxone in the event of an opioid overdose
- To tell family and friends about their naloxone and to keep it in a place where family and friends can access it in an emergency
- To read the Patient Information (or other educational material) that will come with their naloxone. Emphasize the importance of doing this before an opioid emergency happens, so the patient and caregiver will know what to do.

Hyperalgesia and Allodynia

Inform patients and caregivers not to increase opioid dosage without first consulting a clinician. Advise patients to seek medical attention if they experience symptoms of hyperalgesia, including worsening pain, increased sensitivity to pain, or new pain [see Warnings and Precautions (5.7), Adverse Reactions (6.2)].

Serotonin Syndrome

Inform patients that opioids could cause a rare but potentially life-threatening condition resulting from concomitant administration of serotonergic drugs. Warn patients of the symptoms of serotonin syndrome and to seek medical attention right away if symptoms develop. Instruct patients to inform their physicians if they are taking, or plan to take serotonergic medications [see Drug Interactions (7)].

MAOI Interaction

Inform patients to avoid taking hydrocodone bitartrate extended-release capsules while using any drugs that inhibit monoamine oxidase. Patients should not start MAOIs while taking hydrocodone bitartrate extended-release capsules [see Drug Interactions (7)].

Important Administration Instructions [see Dosage and Administration (2)]

Instruct patients how to properly take hydrocodone bitartrate extended-release capsules, including the following:

- Use hydrocodone bitartrate extended-release capsules exactly as prescribed to reduce the risk of life-threatening adverse reactions (e.g., respiratory depression) [see Warnings and Precautions (5.3)].
- Swallow hydrocodone bitartrate extended-release capsules whole.
- Do not crush, chew, or dissolve the capsule or its contents.

Important Discontinuation Instructions

In order to avoid developing withdrawal symptoms, instruct patients not to discontinue hydrocodone bitartrate extended-release capsules without first discussing a tapering plan with the prescriber [see Dosage and Administration (2.6)].

Driving or Operating Heavy Machinery

Inform patients that hydrocodone bitartrate extended-release capsules may impair the ability to perform potentially hazardous activities such as driving a car or operating heavy machinery. Blood levels of hydrocodone, in some patients, may be high at the end of 24 hours after repeated dose administration. Advise patients not to perform such tasks until they know how they will react to the medication [see Warnings and Precautions (5.15)].

Constipation

Advise patients of the potential for severe constipation, including management instructions and when to seek medical attention. Instruct patients to monitor their analgesic response following the use of strong laxatives and to contact the prescriber if changes are noted [see Adverse Reactions (6), Clinical Pharmacology (12.2)].

Adrenal Insufficiency

Inform patients that opioids could cause adrenal insufficiency, a potentially life-threatening condition. Adrenal insufficiency may present with non-specific symptoms and signs such as nausea, vomiting, anorexia, fatigue, weakness, dizziness, and low blood pressure. Advise patients to seek medical attention if they experience a constellation of these symptoms [see Warnings and Precautions (5.9)].

Hypotension

Inform patients that hydrocodone bitartrate extended-release capsules may cause orthostatic hypotension and syncope. Instruct patients how to recognize symptoms of low blood pressure and how to reduce the risk of serious consequences should hypotension occur (e.g., sit or lie down, carefully rise from a sitting or lying position) [see Warnings and Precautions (5.10)].

Anaphylaxis

Inform patients that anaphylaxis has been reported with ingredients contained in hydrocodone bitartrate extended-release capsules. Advise patients how to recognize such a reaction and when to seek medical attention [see Contraindications (4), Adverse Reactions (6)].

Pregnancy

Neonatal Opioid Withdrawal Syndrome

Inform female patients of reproductive potential that use of hydrocodone bitartrate extended-release capsules for an extended period of time during pregnancy can result in neonatal opioid withdrawal syndrome, which may be life-threatening if not recognized and treated [see Warnings and Precautions (5.4), Use in Specific Populations (8.1)].

Embryo-Fetal Toxicity

Inform female patients of reproductive potential that hydrocodone bitartrate extended-release capsules can cause fetal harm and to inform their healthcare provider of a known or suspected pregnancy [see Use in Specific Populations (8.1)].

Lactation

Advise patients that breastfeeding is not recommended during treatment with hydrocodone bitartrate extended-release capsules [see Use in Specific Populations (8.2)].

Infertility

Inform patients that use of opioids for an extended period of time may cause reduced fertility. It is not known whether these effects on fertility are reversible [see Use in Specific Populations (8.3)].

Product of USA

Distributed by:
Alvogen, Inc.
Morristown, NJ 07960 USA

PI409-04

Revised: 12/2023

Medication Guide
Hydrocodone Bitartrate Extended-Release Capsules, CII
(hye" droe koe' done bye tar' trate)

Hydrocodone bitartrate extended-release capsules are:

- A strong prescription pain medicine that contains an opioid (narcotic) that is used to manage severe and persistent pain that requires an extended treatment period with a daily opioid pain medicine when other pain medicines do not treat your pain well enough or you cannot tolerate them.
- A long acting (extended-release) opioid pain medicine that can put you at risk for overdose and death. Even if you take your dose correctly as prescribed, you are at risk for opioid addiction, abuse, and misuse that can lead to death.
- Not to be taken on an “as needed” basis.

Important information about hydrocodone bitartrate extended-release capsules:

- Get emergency help or call 911 right away if you take too much hydrocodone bitartrate extended-release capsules (overdose). When you first start taking hydrocodone bitartrate extended-release capsules, when your dose is changed, or if you take too much (overdose), serious or life-threatening breathing problems that can lead to death may occur. Talk to your healthcare provider about naloxone, a medicine for the emergency treatment of an opioid overdose.
- Taking hydrocodone bitartrate extended-release capsules with other opioid medicines, benzodiazepines, alcohol, or other central nervous system depressants (including street drugs) can cause severe drowsiness, decreased awareness, breathing problems, coma, and death.
- Never give anyone else your hydrocodone bitartrate extended-release capsules. They could die from taking it. Selling or giving away hydrocodone bitartrate extended-release capsules is against the law.
- Store hydrocodone bitartrate extended-release capsules securely, out of sight and reach of children, and in a location not accessible by others, including visitors to the home.

Do not take hydrocodone bitartrate extended-release capsules if you have:

- severe asthma, trouble breathing, or other lung problems.
- a bowel blockage or narrowing of the stomach or intestines.

Before taking hydrocodone bitartrate extended-release capsules, tell your healthcare provider if you have a history of:

- head injury, seizures
- problems urinating
- liver, kidney, thyroid problems
- pancreas or gallbladder problems
- abuse of street or prescription drugs, alcohol addiction, opioid overdose, or mental health problems.

Tell your healthcare provider if you:

- are noticing your pain getting worse. If your pain gets worse after you take hydrocodone bitartrate extended-release capsules, do not take more of hydrocodone bitartrate extended-release capsules without first talking to your healthcare provider. Talk to your healthcare provider if the pain that you have increases, if you feel more sensitive to pain, or if you have new pain after taking hydrocodone bitartrate extended-release capsules.
- are pregnant or planning to become pregnant. Use of hydrocodone bitartrate extended-release capsules for an extended period of time during pregnancy can cause withdrawal symptoms in your newborn baby that could be life-threatening if not recognized and treated.
- are breastfeeding. Not recommended during treatment with hydrocodone bitartrate extended-release capsules. It may harm your baby.
- are living in a household where there are small children or someone who has abused street or prescription drugs.
- are taking prescription or over-the-counter medicines, vitamins, or herbal supplements. Taking hydrocodone bitartrate extended-release capsules with certain other medicines can cause serious side effects that could lead to death.

When taking hydrocodone bitartrate extended-release capsules:

- Do not change your dose. Take hydrocodone bitartrate extended-release capsules exactly as prescribed by your healthcare provider. Use the lowest dose possible for the shortest time needed.
- Take your prescribed dose every 12 hours, at the same time every day. Do not take more than your prescribed dose in 12 hours. If you miss a dose, take your next dose at your usual time.
- Swallow hydrocodone bitartrate extended-release capsules whole. Do not cut, break, chew, crush, dissolve, snort, or inject hydrocodone bitartrate extended-release capsules because this may cause you to overdose and die.

Call your healthcare provider if the dose you are taking does not control your pain.

- Do not stop taking hydrocodone bitartrate extended-release capsules without talking to your healthcare provider.
- Dispose of expired, unwanted, or unused hydrocodone bitartrate extended-release capsules by taking your drug to an authorized DEA-registered collector or drug take-back program. If one is not available, you can dispose of hydrocodone bitartrate extended-release capsules by mixing the product with dirt, cat litter, or coffee grounds; placing the mixture in a sealed plastic bag, and throwing the bag in your trash. Visit www.fda.gov/drugdisposal for additional information on disposal of unused medicines.

While taking hydrocodone bitartrate extended-release capsules DO NOT:

- Drive or operate heavy machinery, until you know how hydrocodone bitartrate extended-release capsules affects you. Hydrocodone bitartrate extended-release capsules can make you sleepy, dizzy, or lightheaded.
- Drink alcohol or use prescription or over-the-counter medicines that contain alcohol. Using products containing alcohol during treatment with hydrocodone bitartrate extended-release capsules may cause you to overdose and die.

The possible side effects of hydrocodone bitartrate extended-release capsules are:

- constipation, nausea, sleepiness, vomiting, tiredness, headache, dizziness, abdominal pain. Call your healthcare provider if you have any of these symptoms and they are severe.

Get emergency medical help or call 911 right away if you have:

- trouble breathing, shortness of breath, fast heartbeat, chest pain, swelling of your face, tongue or throat, extreme drowsiness, light-headedness when you are changing positions, feeling faint, agitation, high body temperature, trouble walking, stiff muscles, or mental changes such as confusion.

These are not all the possible side effects of hydrocodone bitartrate extended-release capsules. Call your healthcare provider for medical advice about side effects. You may report side effects to FDA at 1-800-FDA-1088. For more information go to dailymed.nlm.nih.gov.
Product of USA
Distributed by:
Alvogen, Inc.
Morristown, NJ 07960 USA
For more information, call Alvogen at 1-866-770-3024.

This Medication Guide has been approved by the U.S. Food and Drug Administration

Revised: 12/2023
PL409-04

PRINCIPAL DISPLAY PANEL - 10 mg Capsule Bottle Label

NDC 47781-409-60
Hydrocodone Bitartrate Extended-Release Capsules CII

10 mg

PHARMACIST: Dispense the Medication Guide provided separately to each patient.

Swallow capsules whole.
Do not chew, crush, or dissolve.

60 Capsules
Rx only

PRINCIPAL DISPLAY PANEL - 15 mg Capsule Bottle Label

NDC 47781-410-60
Hydrocodone Bitartrate Extended-Release Capsules CII
15 mg
PHARMACIST: Dispense the Medication Guide provided separately to each patient.

Swallow capsules whole.
Do not chew, crush, or dissolve.
60 Capsules
Rx only

PRINCIPAL DISPLAY PANEL - 20 mg Capsule Bottle Label

NDC 47781-411-60
Hydrocodone Bitartrate Extended-Release Capsules CII

20 mg

PHARMACIST: Dispense the Medication Guide provided separately to each patient.

Swallow capsules whole.
Do not chew, crush, or dissolve.

60 Capsules
Rx only

PRINCIPAL DISPLAY PANEL - 30 mg Capsule Bottle Label

NDC 47781-412-60
Hydrocodone Bitartrate Extended-Release Capsules CII

30 mg

PHARMACIST: Dispense the Medication Guide provided separately to each patient.

Swallow capsules whole.
Do not chew, crush, or dissolve.

60 Capsules
Rx only

PRINCIPAL DISPLAY PANEL - 40 mg Capsule Bottle Label

NDC 47781-413-60
Hydrocodone Bitartrate Extended-Release Capsules CII

40 mg

PHARMACIST: Dispense the Medication Guide provided separately to each patient.

Swallow capsules whole.
Do not chew, crush, or dissolve.

60 Capsules
Rx only

PRINCIPAL DISPLAY PANEL - 50 mg Capsule Bottle Label

NDC 47781-414-60
Hydrocodone Bitartrate Extended-Release Capsules CII
50 mg

PHARMACIST: Dispense the Medication Guide provided separately to each patient.

Swallow capsules whole.
Do not chew, crush, or dissolve.

60 Capsules
Rx only